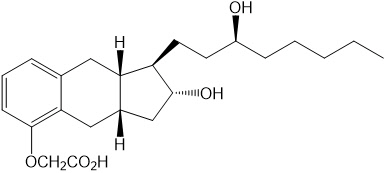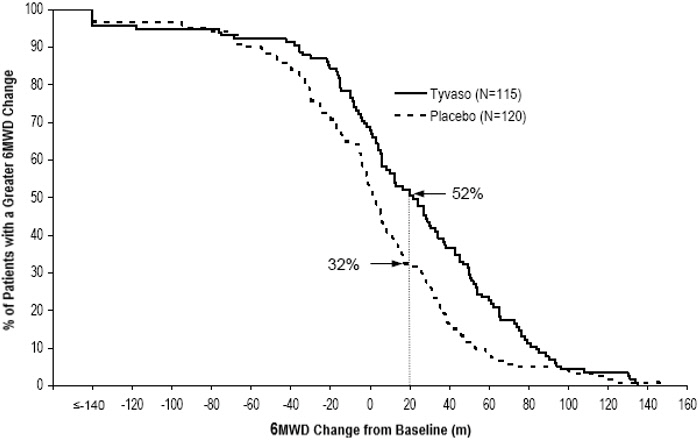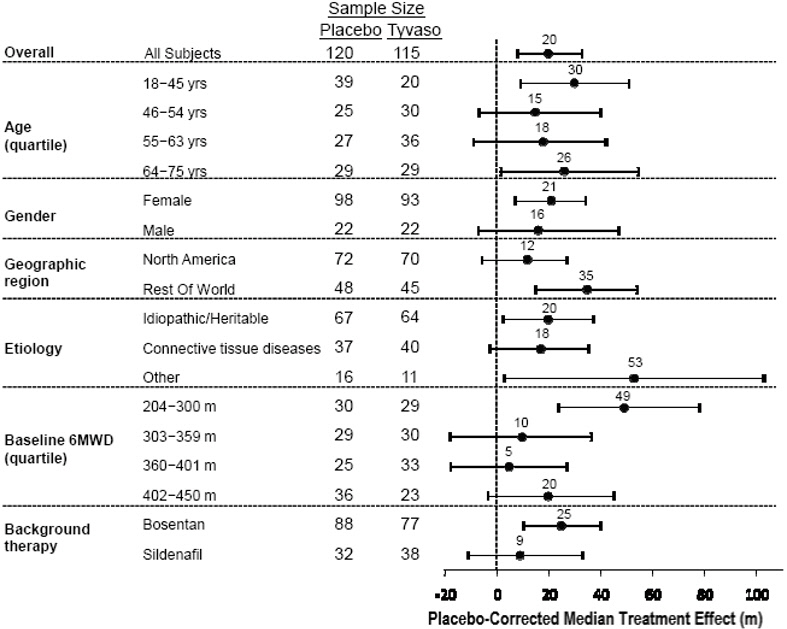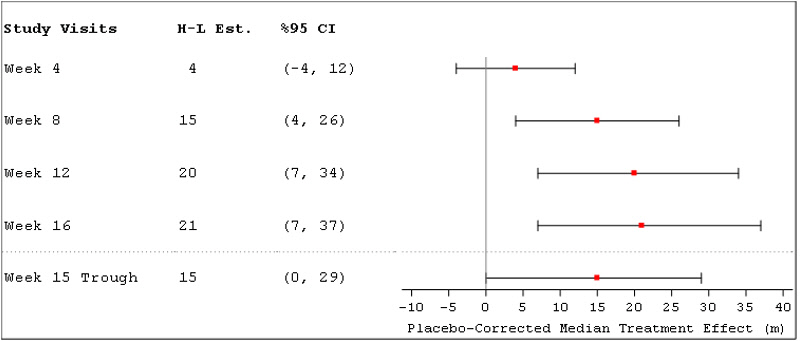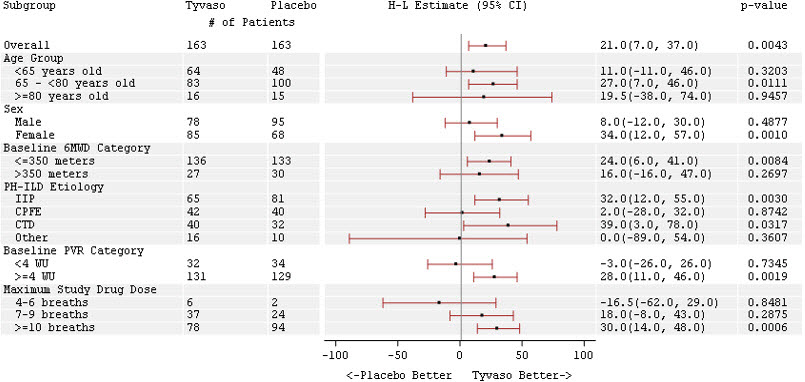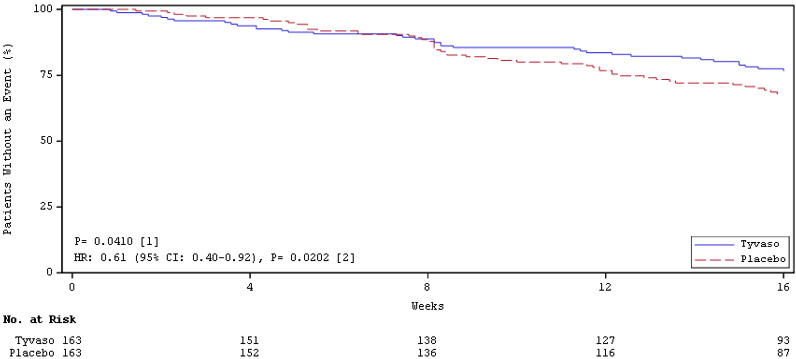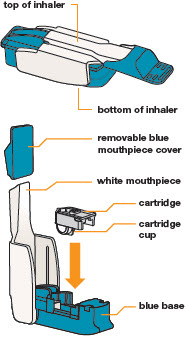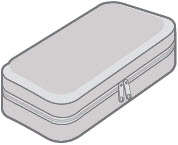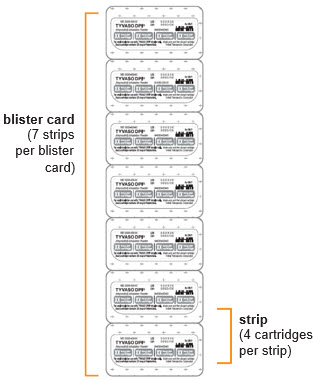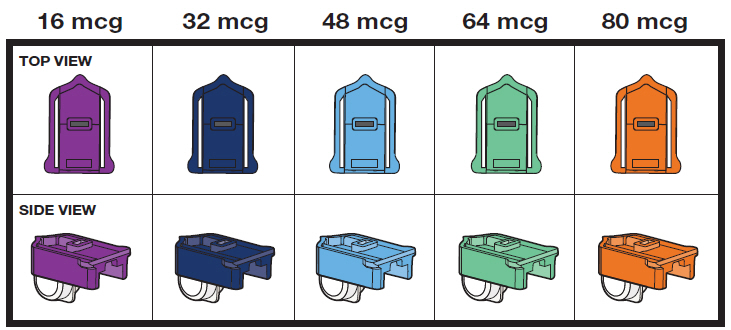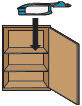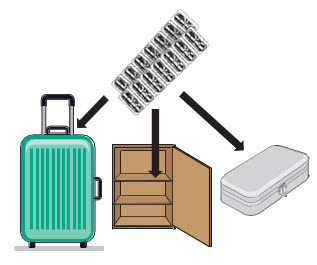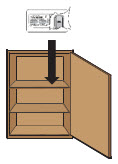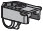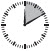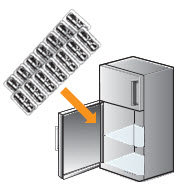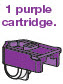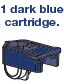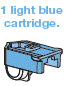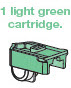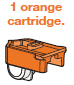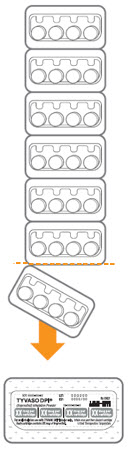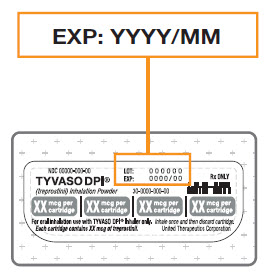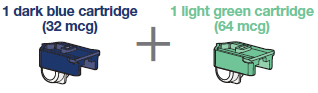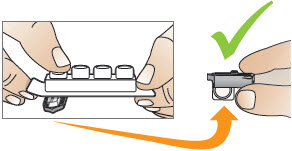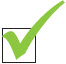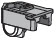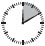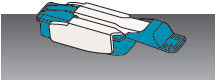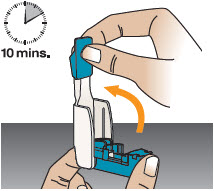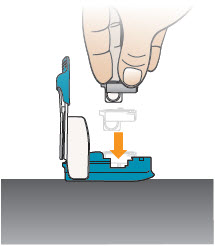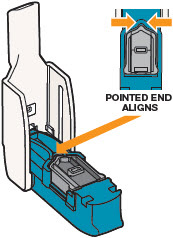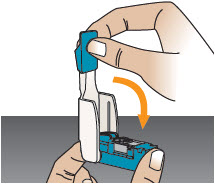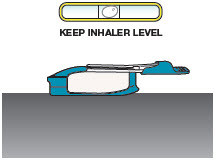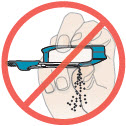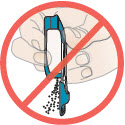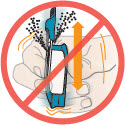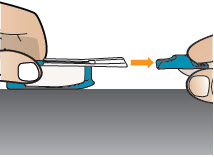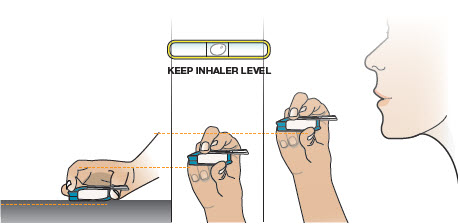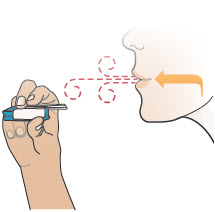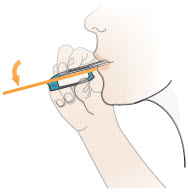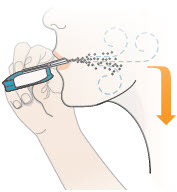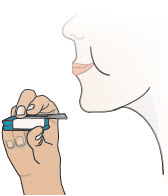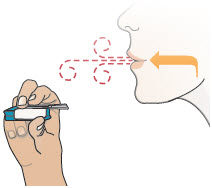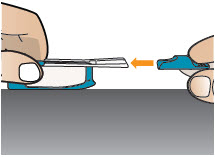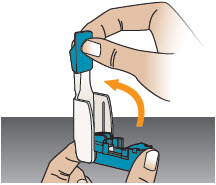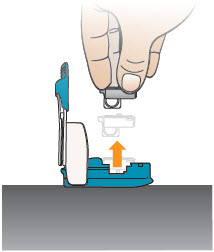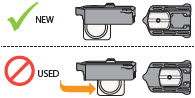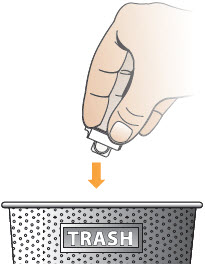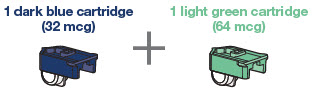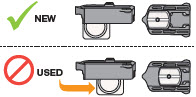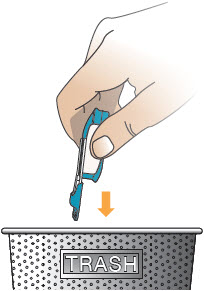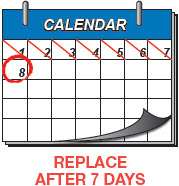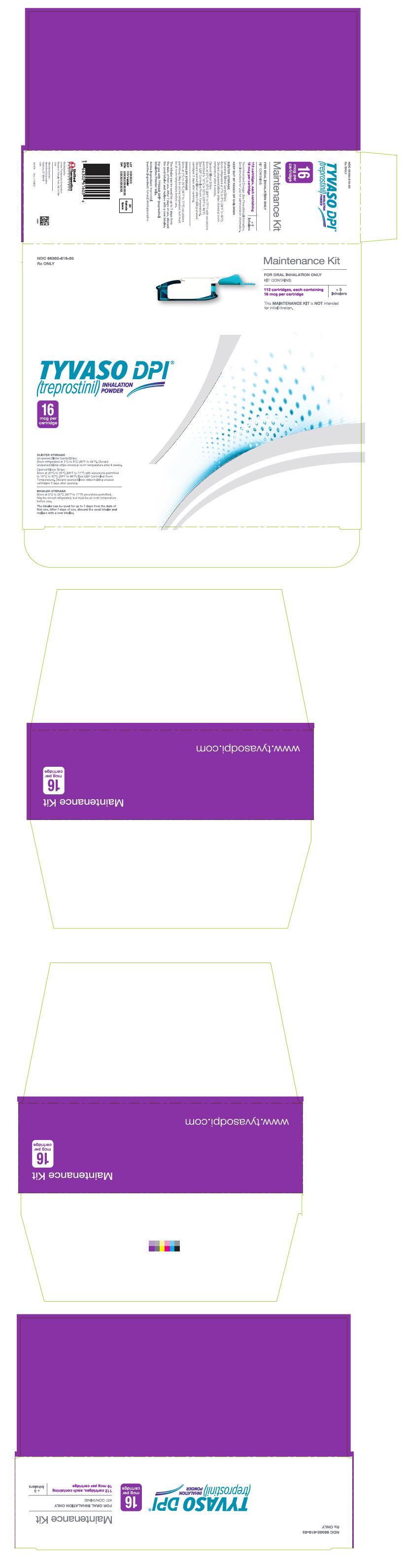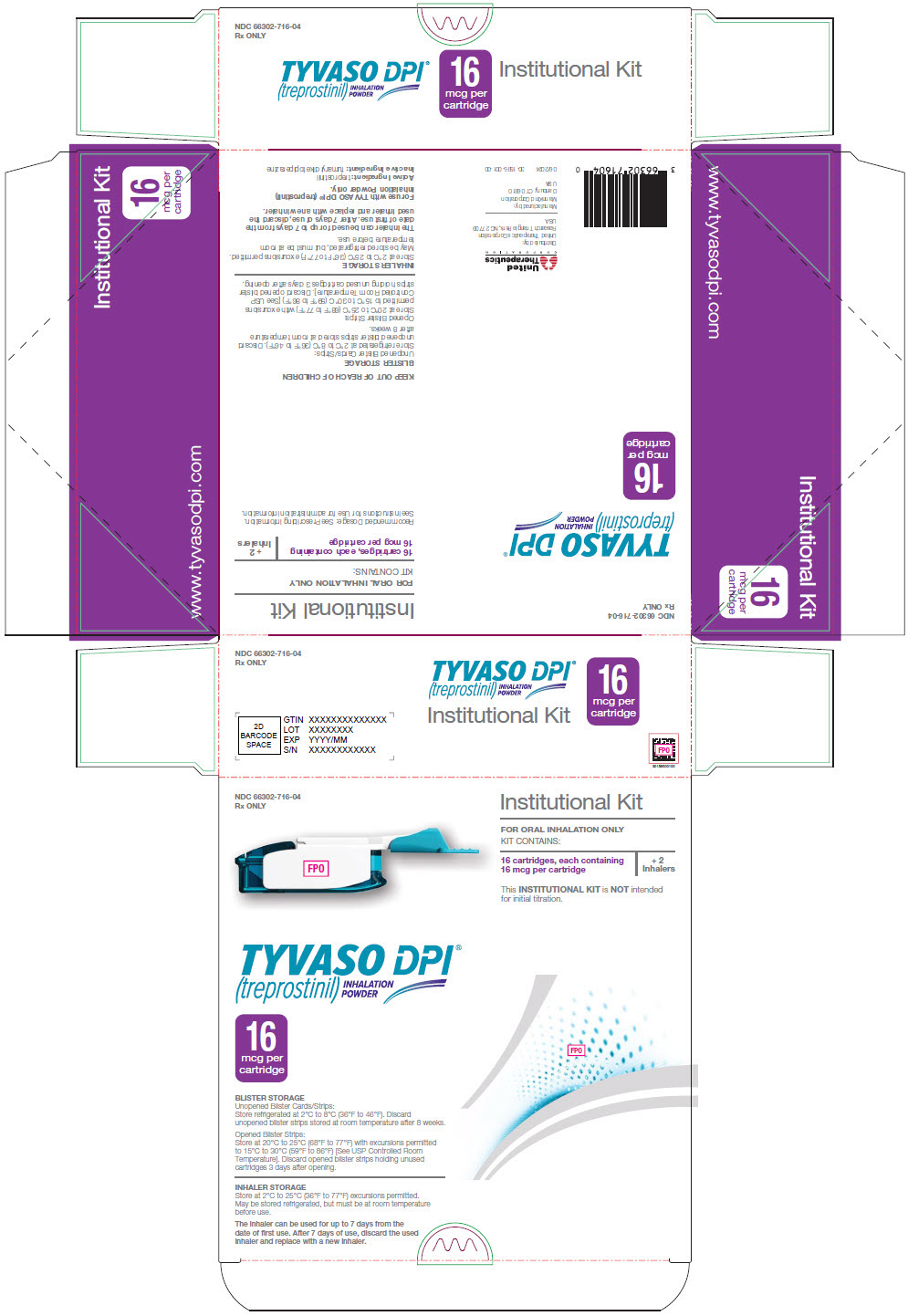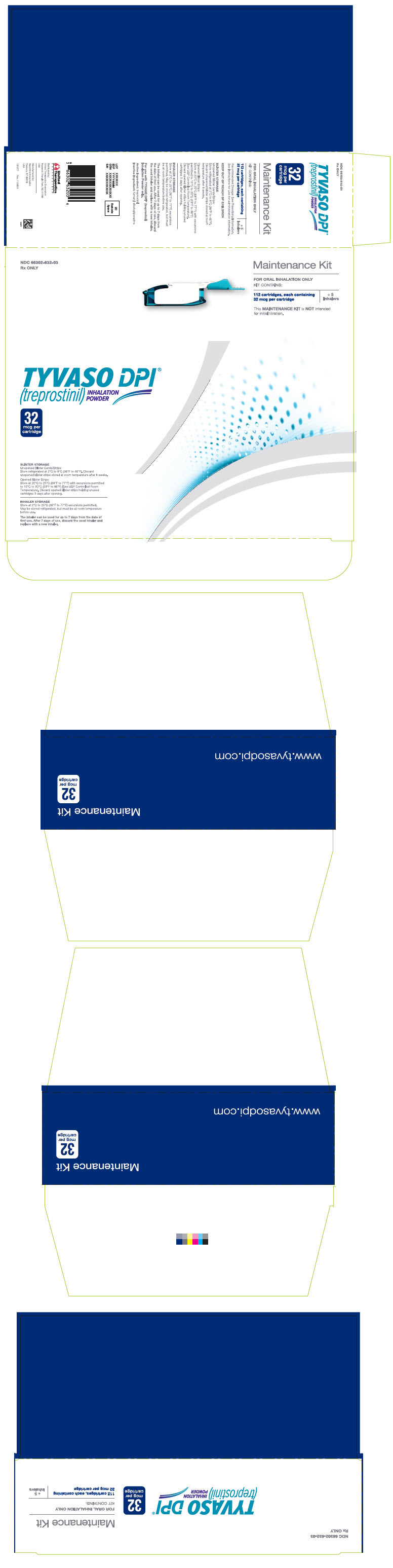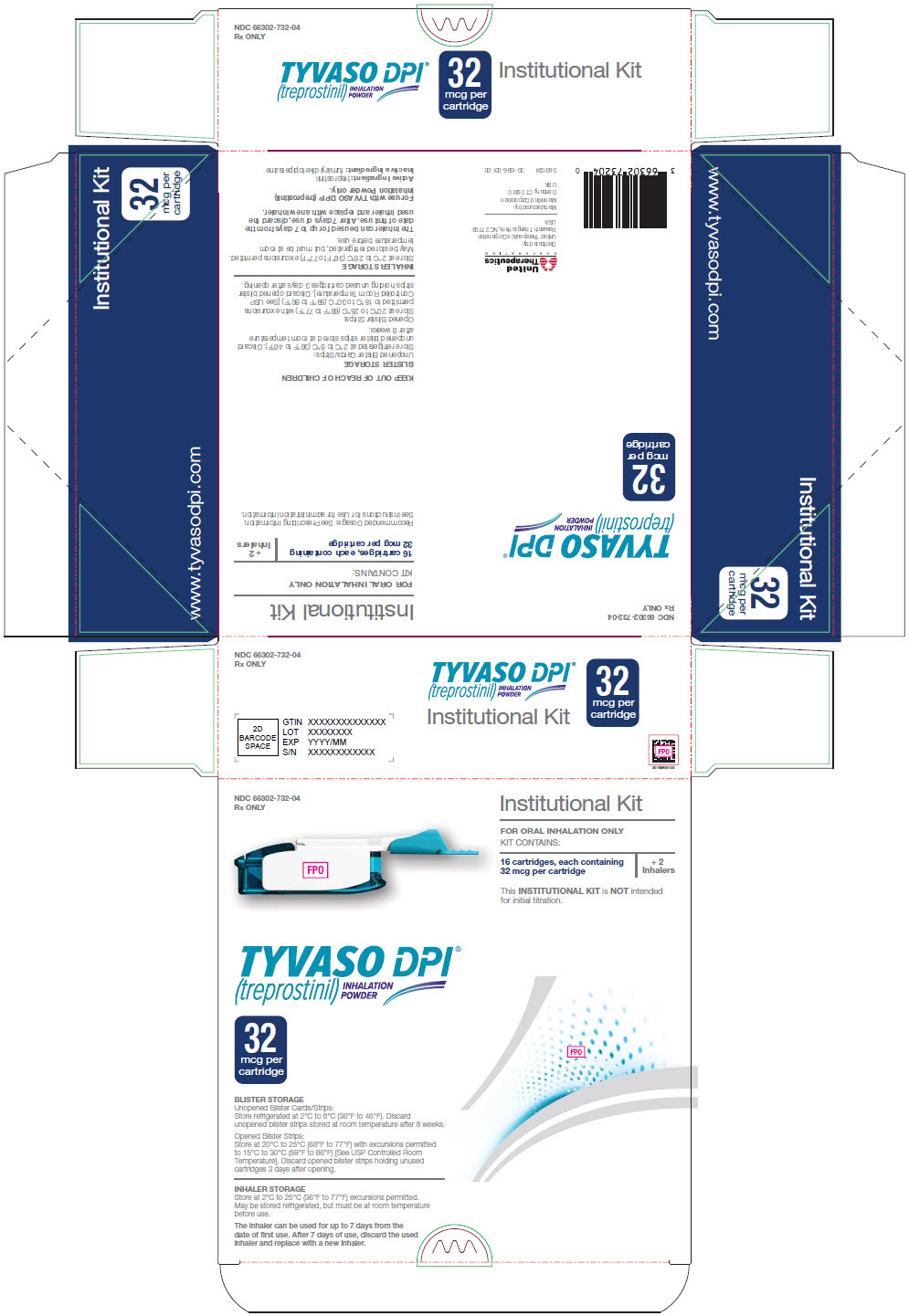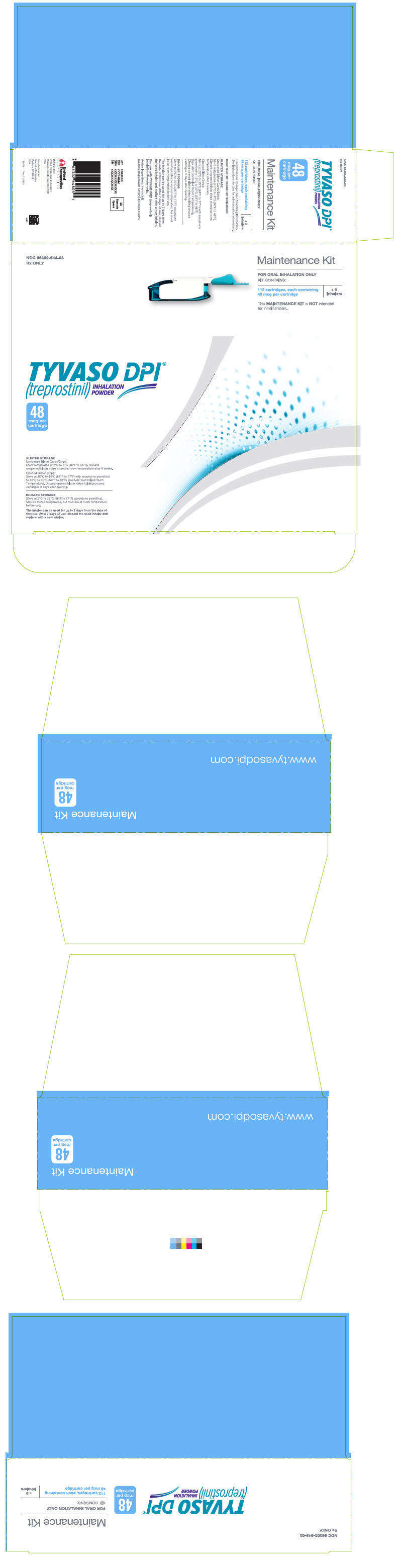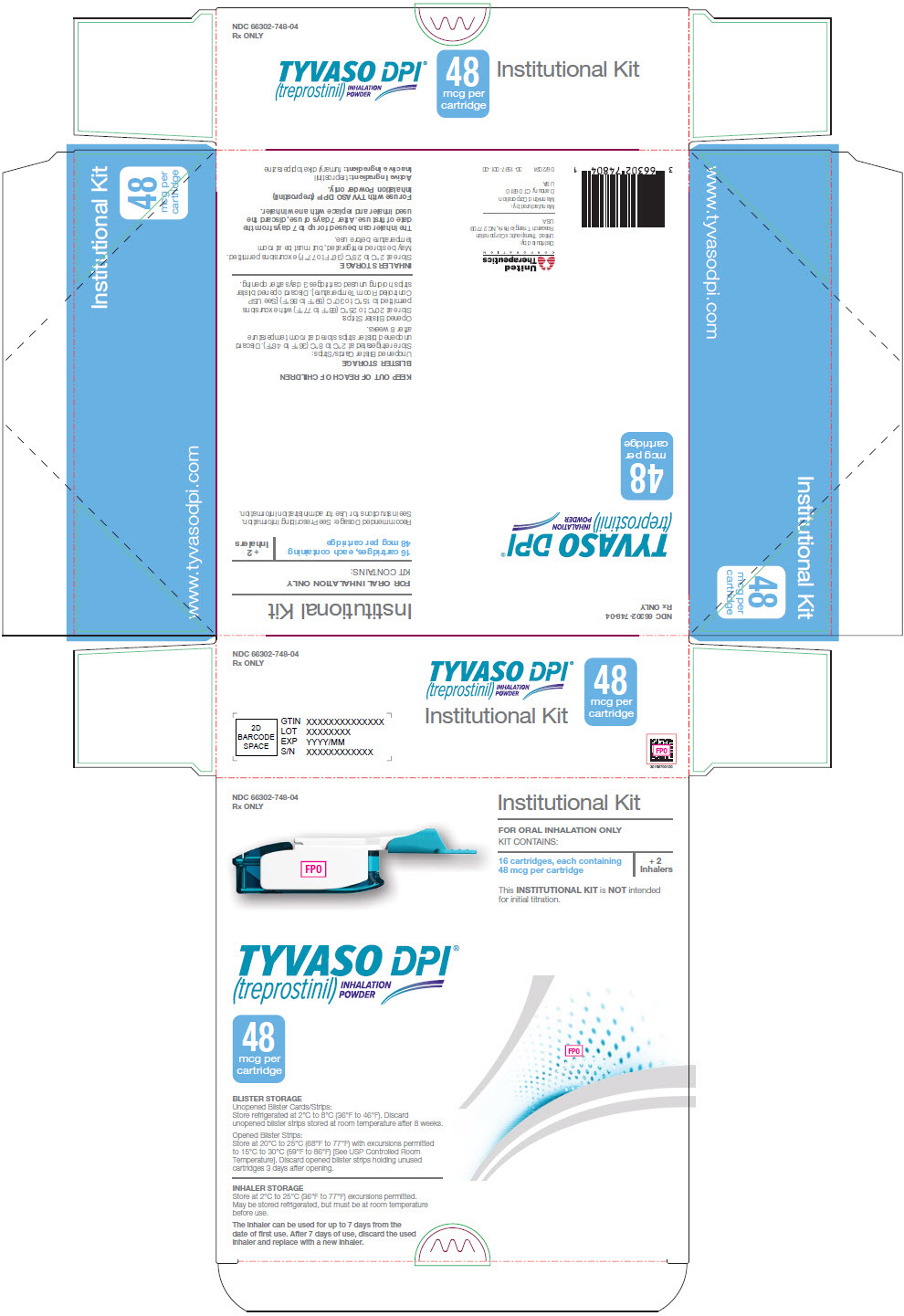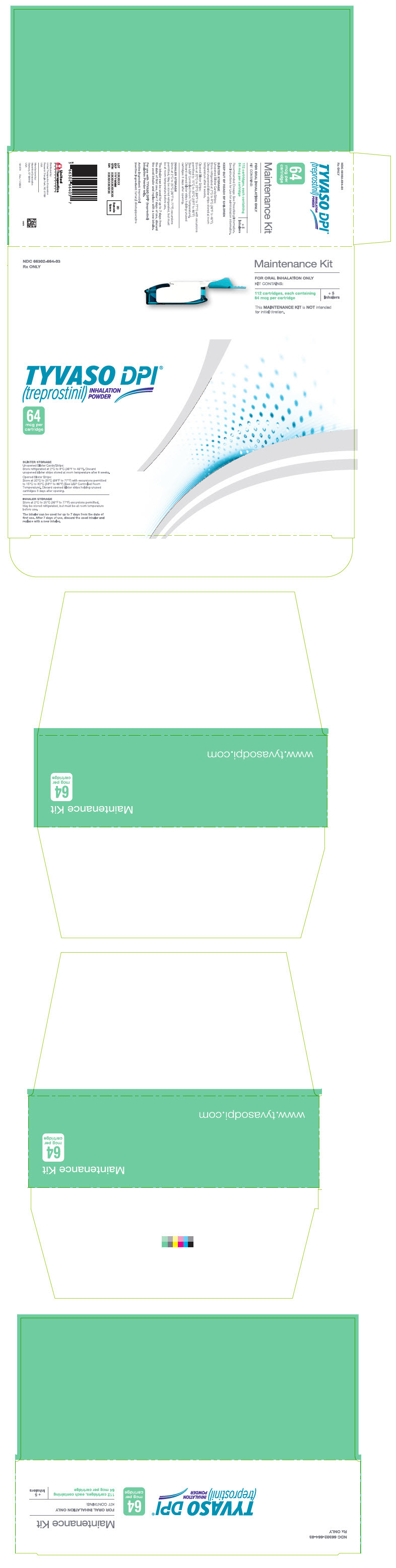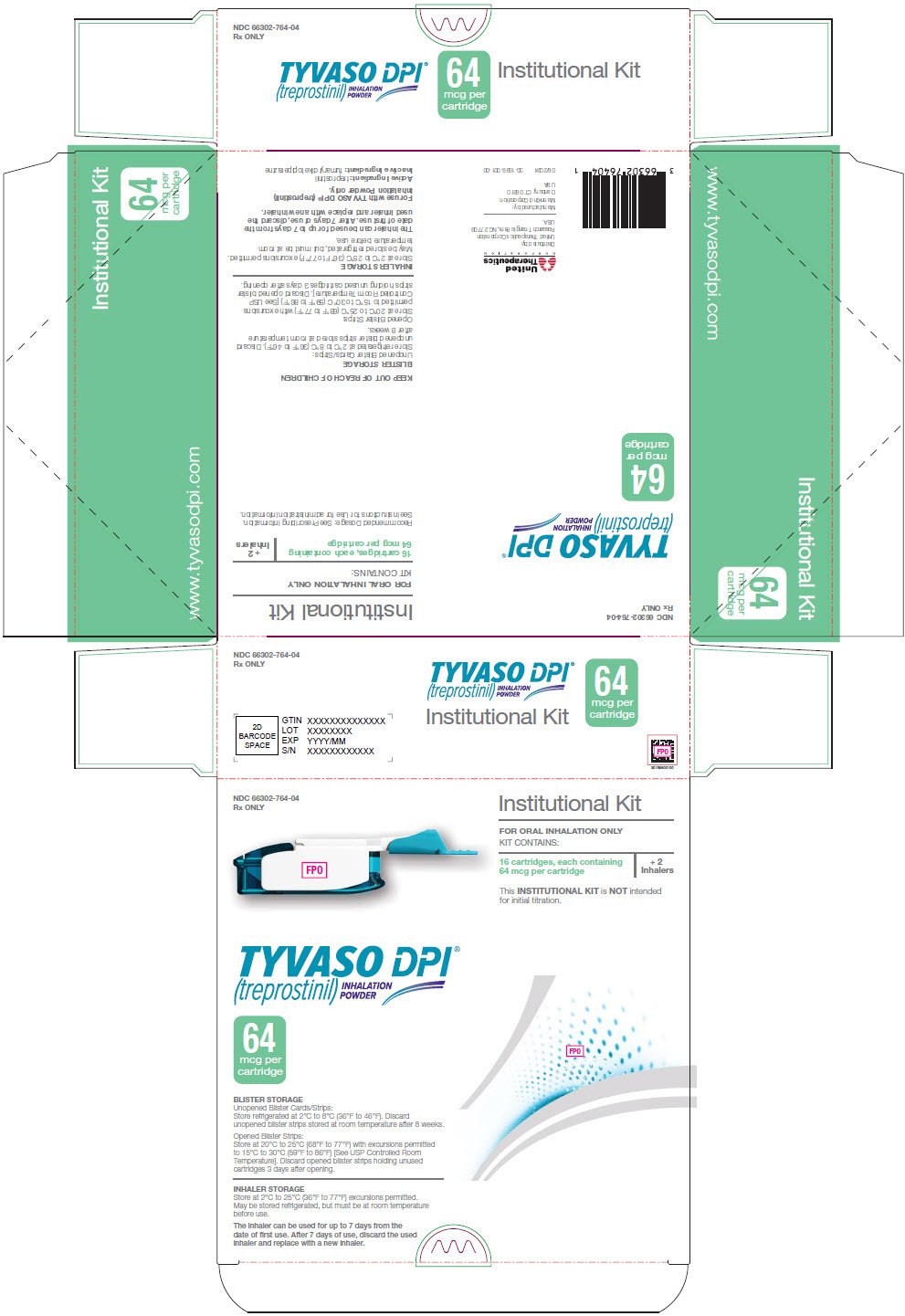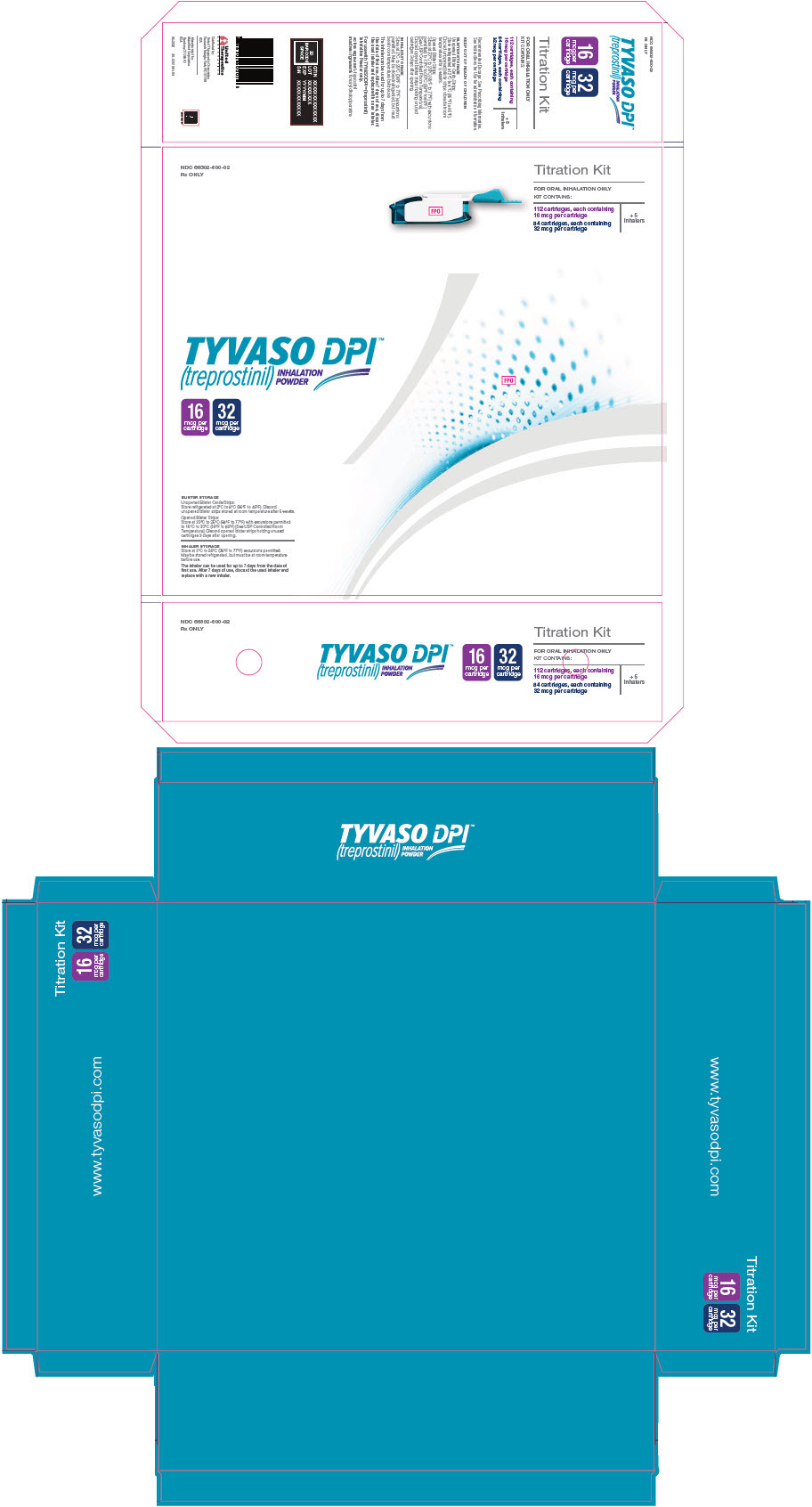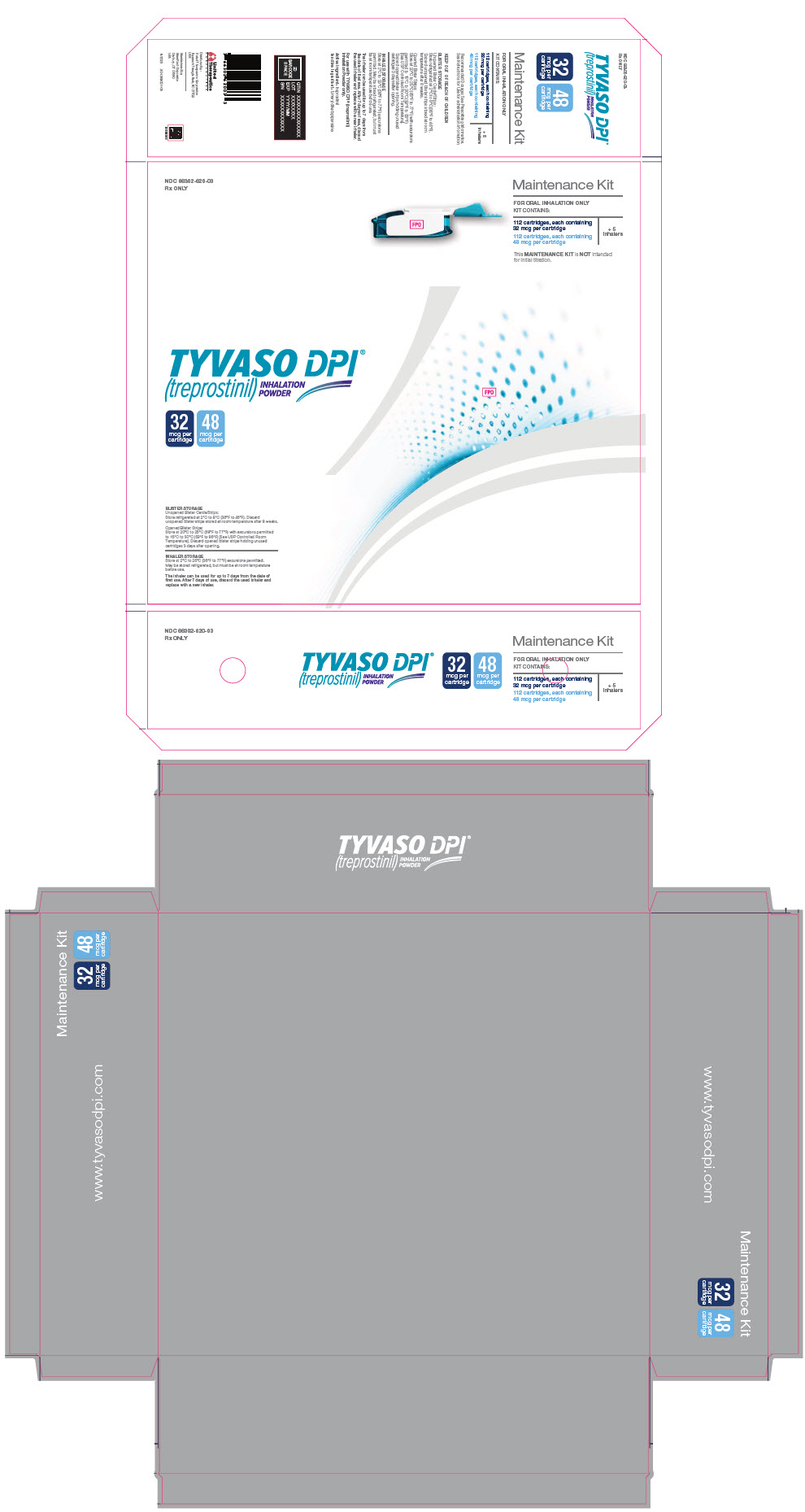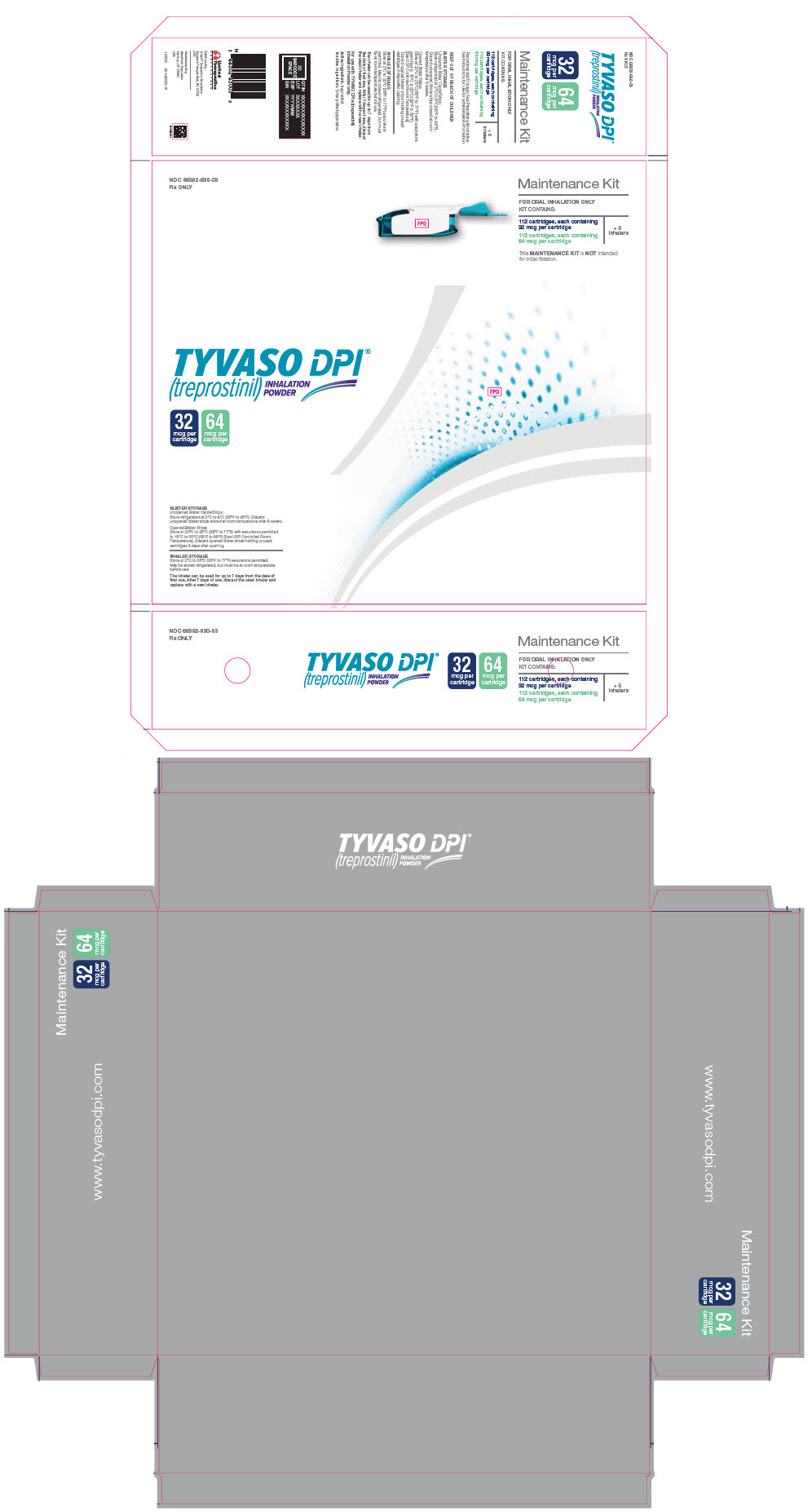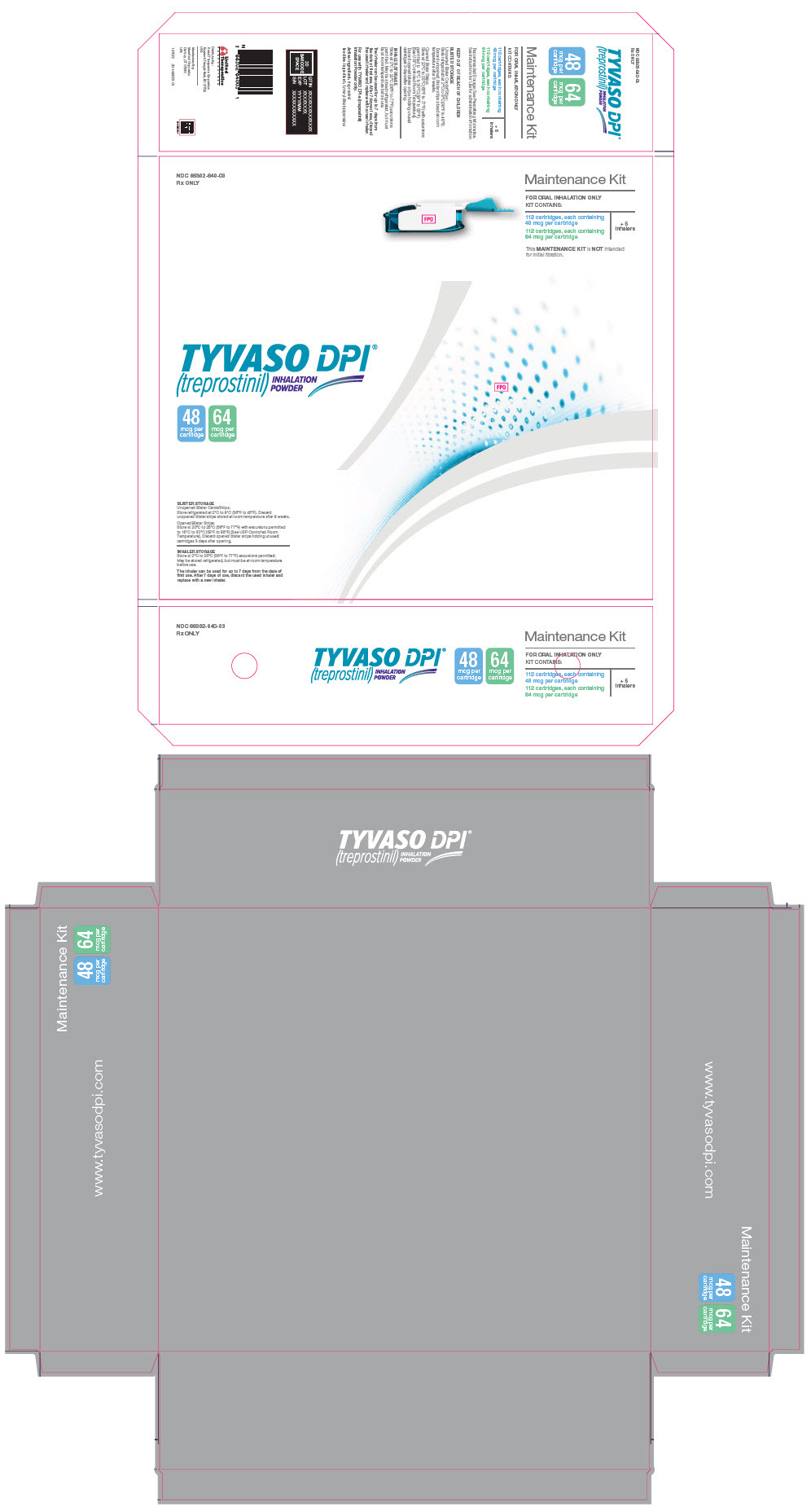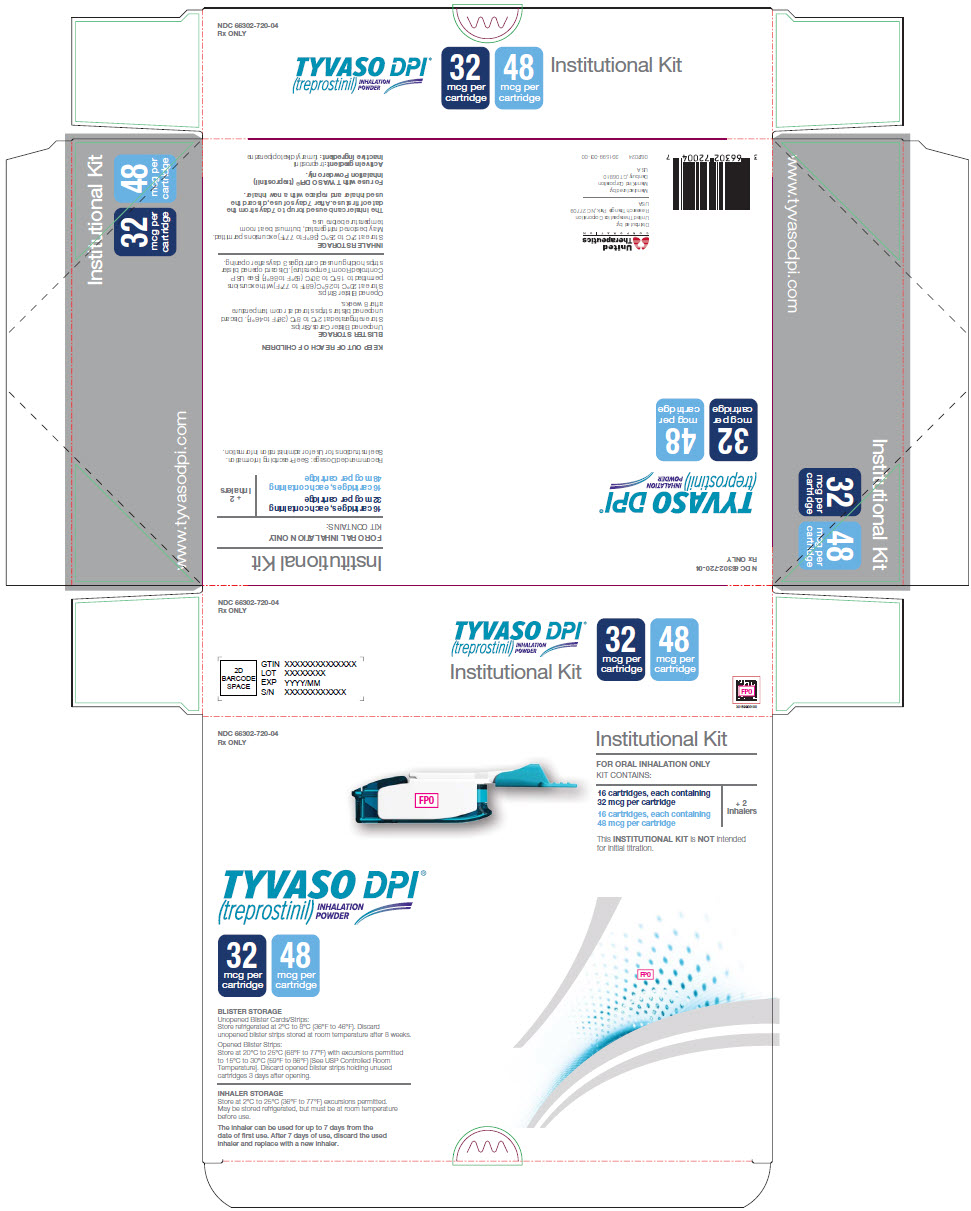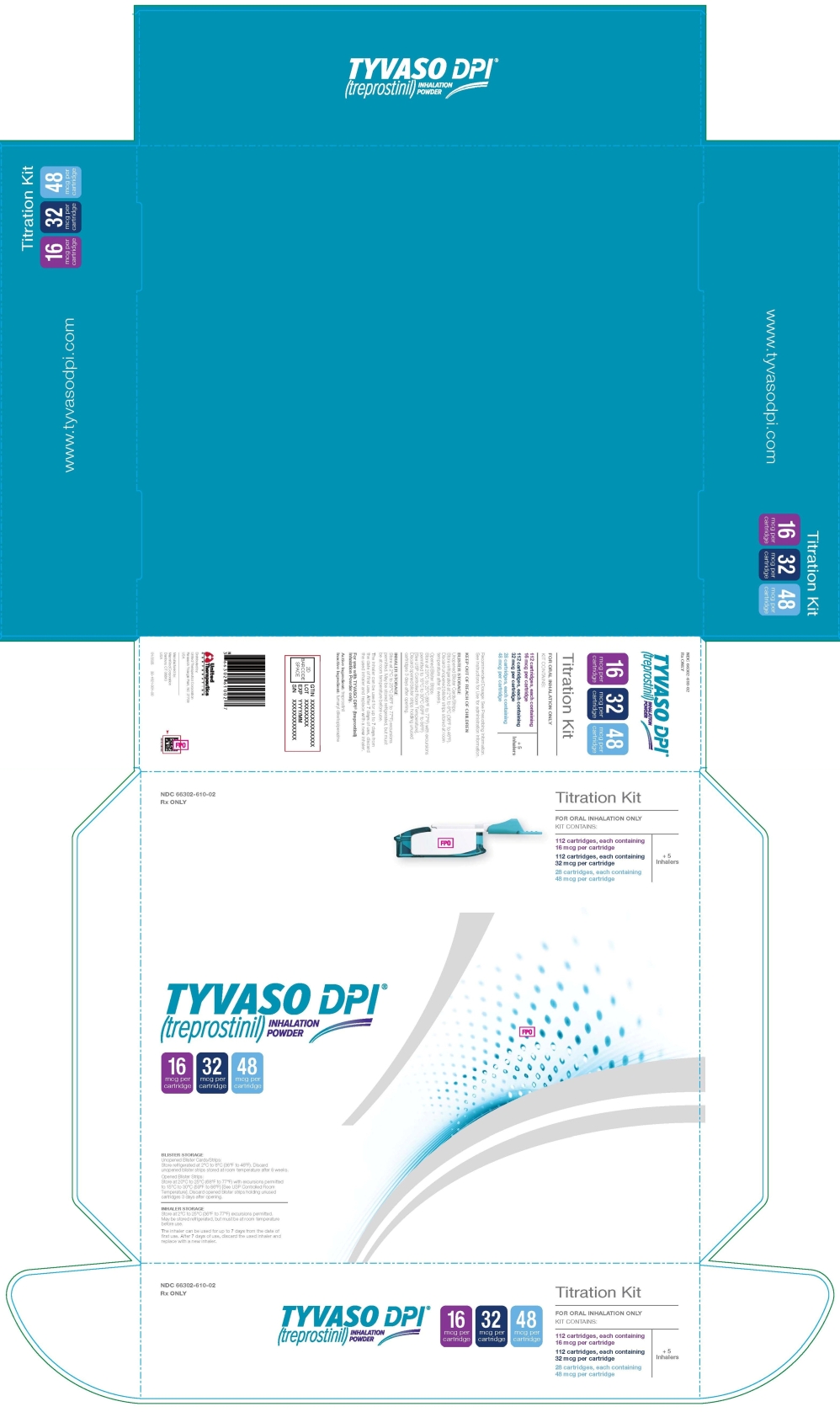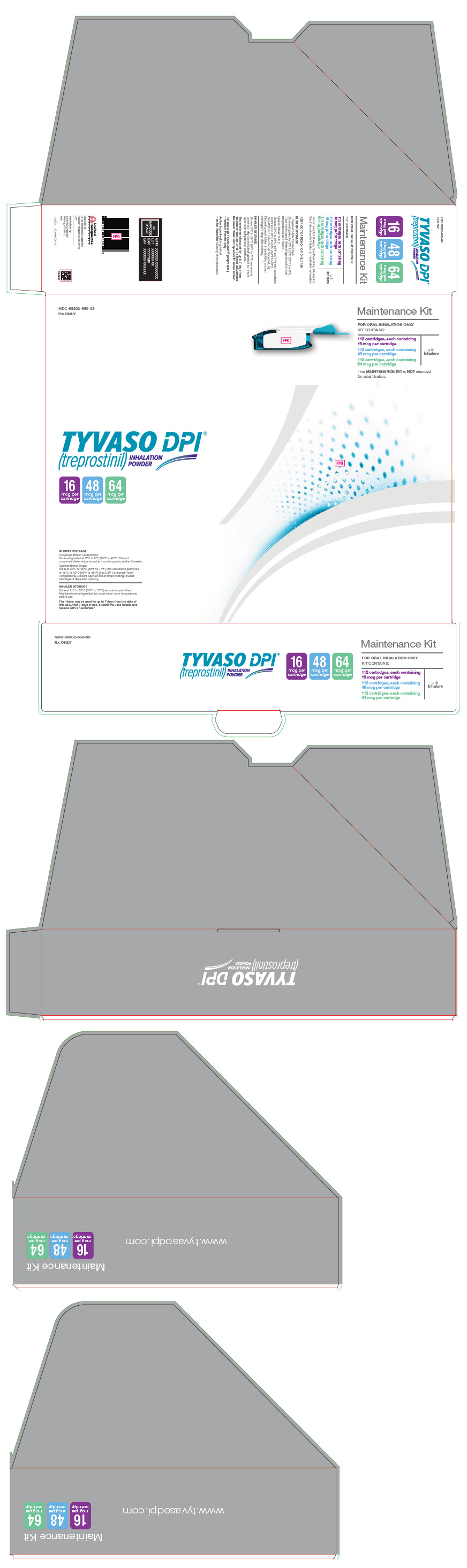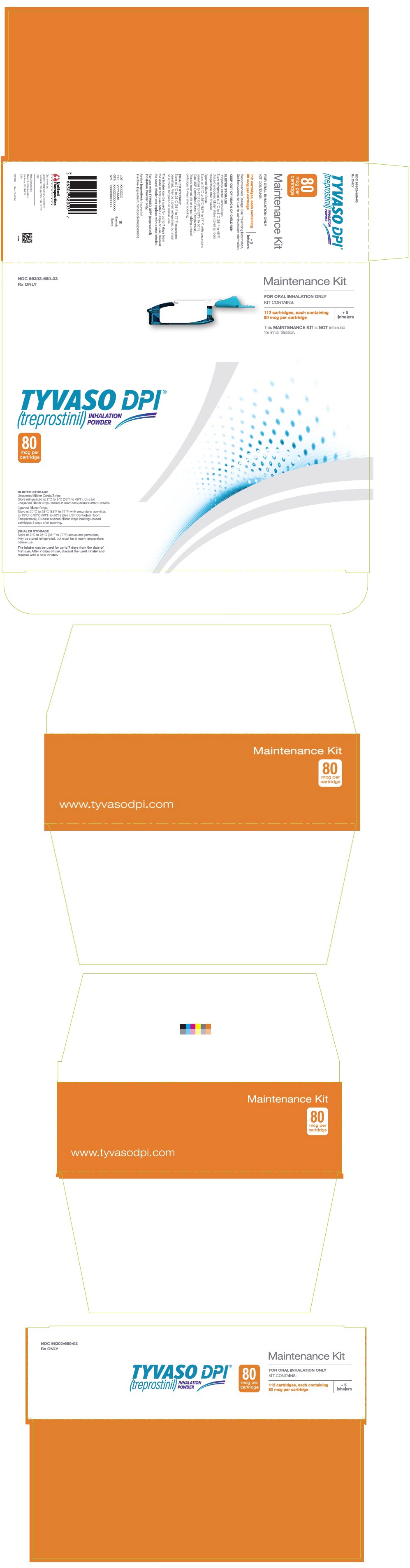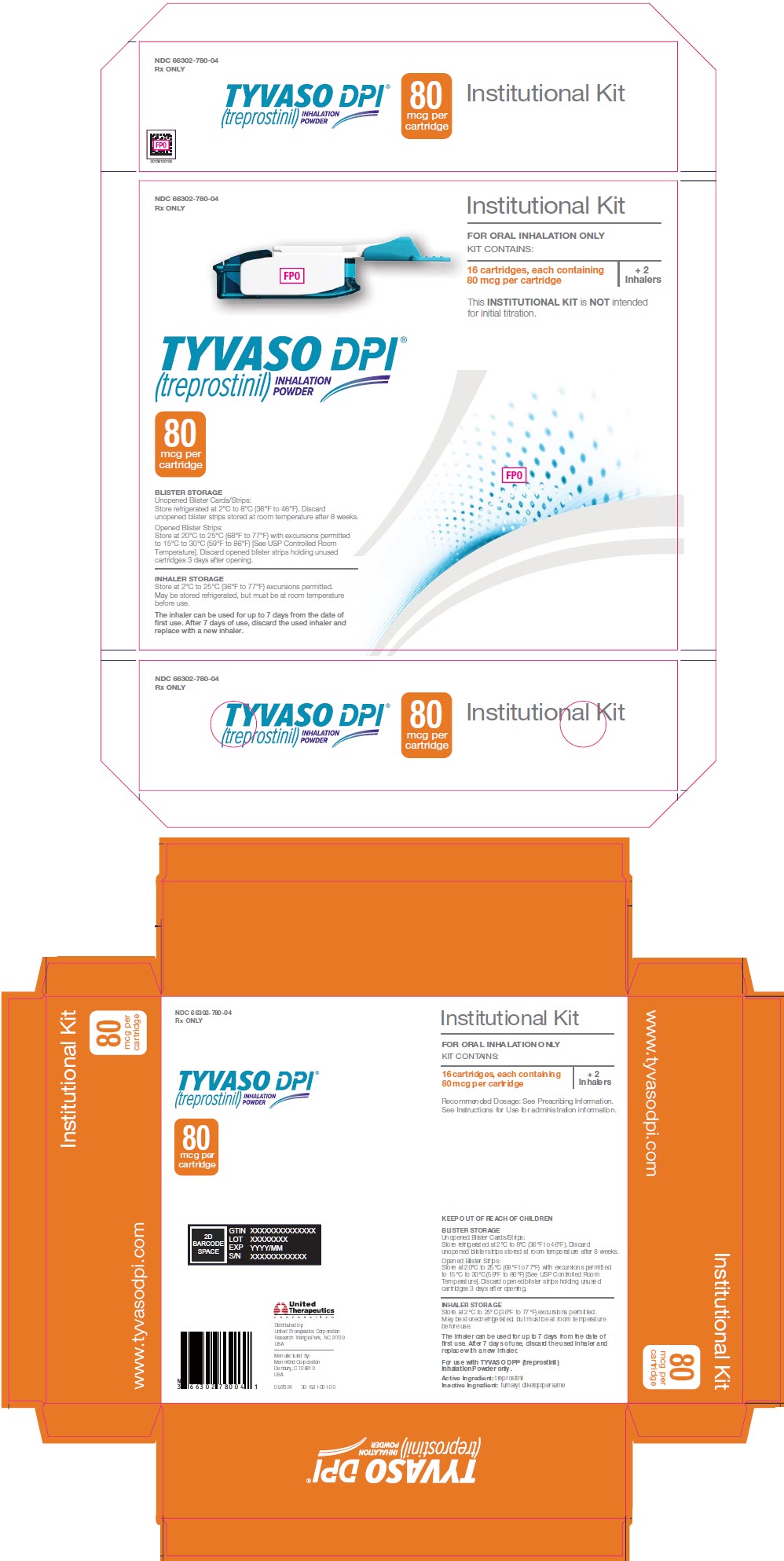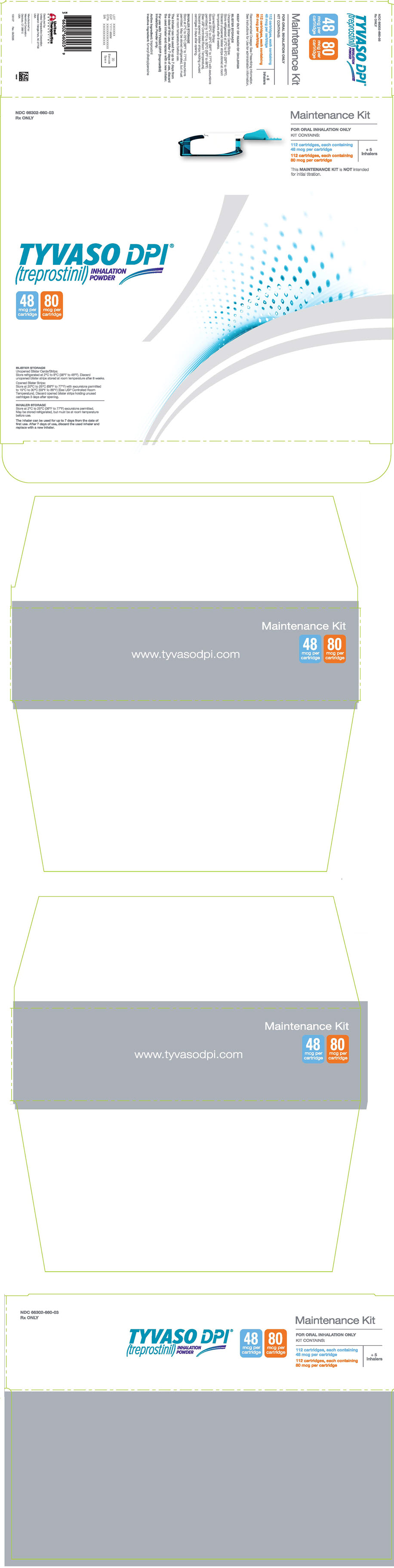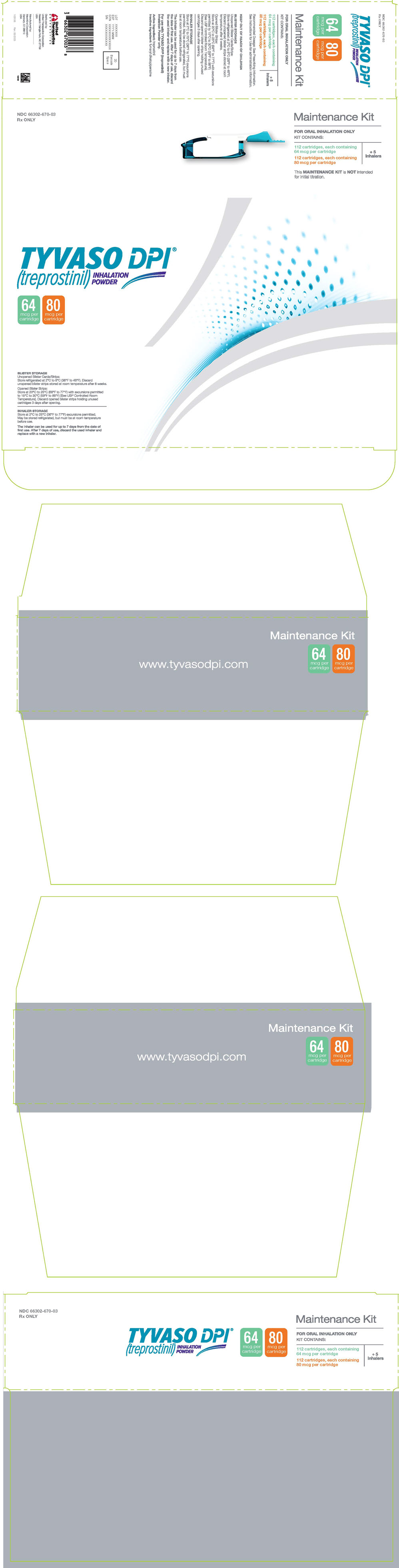 DRUG LABEL: Tyvaso DPI
NDC: 66302-616 | Form: INHALANT
Manufacturer: United Therapeutics Corporation
Category: prescription | Type: HUMAN PRESCRIPTION DRUG LABEL
Date: 20251120

ACTIVE INGREDIENTS: TREPROSTINIL 16 ug/1 1
INACTIVE INGREDIENTS: FUMARYL DIKETOPIPERAZINE

HIGHLIGHTS OF PRESCRIBING INFORMATION

These highlights do not include all the information needed to use TYVASO DPI safely and effectively. See full prescribing information for TYVASO DPI.
TYVASO DPI® (treprostinil) inhalation powder, for oral inhalation use
Initial U.S. Approval: 2002

1 INDICATIONS AND USAGE

Tyvaso DPI is a prostacyclin mimetic indicated for the treatment of:

- Pulmonary arterial hypertension (PAH; WHO Group 1) to improve exercise ability. Studies with Tyvaso establishing effectiveness predominately included patients with NYHA Functional Class III symptoms and etiologies of idiopathic or heritable PAH (56%) or PAH associated with connective tissue diseases (33%). (1.1)
- Pulmonary hypertension associated with interstitial lung disease (PH-ILD; WHO Group 3) to improve exercise ability. The study with Tyvaso establishing effectiveness predominately included patients with etiologies of idiopathic interstitial pneumonia (IIP) (45%) inclusive of idiopathic pulmonary fibrosis (IPF), combined pulmonary fibrosis and emphysema (CPFE) (25%), and WHO Group 3 connective tissue disease (22%). (1.2)

2 DOSAGE AND ADMINISTRATION

- Use only with the Tyvaso DPI Inhaler. (2.1)
- Administer using a single inhalation per cartridge. (2.1)
- Administer in 4 separate treatment sessions each day approximately 4 hours apart, during waking hours. (2.1)
- Initial dosage: one 16 mcg cartridge per treatment session. (2.2)
- Dosage should be increased by an additional 16 mcg per treatment session at approximately 1- to 2-week intervals, if tolerated. (2.2)
- Titrate to target maintenance doses of 48 mcg to 64 mcg per treatment session, 4 times daily. (2.2)

3 DOSAGE FORMS AND STRENGTHS

Inhalation powder: Single-dose plastic cartridges containing 16 mcg, 32 mcg, 48 mcg, 64 mcg, or 80 mcg of treprostinil as a dry powder formulation. (3)

4 CONTRAINDICATIONS

None. (4)

5 WARNINGS AND PRECAUTIONS

- Tyvaso DPI may cause symptomatic hypotension. (5.1)
- Tyvaso DPI inhibits platelet aggregation and increases the risk of bleeding. (5.2)
- Tyvaso DPI dosage adjustments may be necessary if inhibitors or inducers of CYP2C8 are added or withdrawn. (5.3, 7.3)
- May cause bronchospasm: Patients with a history of hyperreactive airway disease may be more sensitive. (5.4)

6 ADVERSE REACTIONS

Most common adverse reactions (≥4%) are cough, headache, throat irritation/pharyngolaryngeal pain, nausea, flushing, dyspnea, and syncope. (6.1)

To report SUSPECTED ADVERSE REACTIONS, contact United Therapeutics Corp. at 1-866-458-6479 or FDA at 1-800-FDA-1088 or www.fda.gov/medwatch.

FULL PRESCRIBING INFORMATION

1 INDICATIONS AND USAGE

1.1 Pulmonary Arterial Hypertension

Tyvaso DPI is indicated for the treatment of pulmonary arterial hypertension (PAH; WHO Group 1) to improve exercise ability. Studies with Tyvaso establishing effectiveness predominately included patients with NYHA Functional Class III symptoms and etiologies of idiopathic or heritable PAH (56%) or PAH associated with connective tissue diseases (33%).

The effects diminish over the minimum recommended dosing interval of 4 hours; treatment timing can be adjusted for planned activities.

While there are long-term data on use of treprostinil by other routes of administration, nearly all clinical experience with inhaled treprostinil has been on a background of an endothelin receptor antagonist (ERA) and/or a phosphodiesterase type 5 (PDE-5) inhibitor. The controlled clinical experience with Tyvaso was limited to 12 weeks in duration [see Clinical Studies (14)].

1.2 Pulmonary Hypertension Associated with ILD

Tyvaso DPI is indicated for the treatment of pulmonary hypertension associated with interstitial lung disease (PH-ILD; WHO Group 3) to improve exercise ability. The study with Tyvaso establishing effectiveness predominately included patients with etiologies of idiopathic interstitial pneumonia (IIP) (45%) inclusive of idiopathic pulmonary fibrosis (IPF), combined pulmonary fibrosis and emphysema (CPFE) (25%), and WHO Group 3 connective tissue disease (22%) [see Clinical Studies (14.3)].

2 DOSAGE AND ADMINISTRATION

2.1 Administration

Use Tyvaso DPI only with the Tyvaso DPI Inhaler. Tyvaso DPI is administered using a single inhalation per cartridge. Administer Tyvaso DPI in 4 separate, equally spaced treatment sessions per day, during waking hours. The treatment sessions should be approximately 4 hours apart.

If the prescribed dose is higher than 80 mcg per treatment session, more than 1 cartridge will be needed per session. Patients should follow the instructions for use for operation and care of the Tyvaso DPI Inhaler.

Do not use the Tyvaso DPI Inhaler with other medications.

Between each of the 4 daily treatment sessions, store the Tyvaso DPI Inhaler with the mouthpiece attached and empty. Wipe the outside of the inhaler with a clean, dry cloth only, if needed. Do not rinse or wash the Tyvaso DPI Inhaler; always keep the inhaler dry. After 7 days of use, throw away the used Tyvaso DPI Inhaler into regular household trash.

2.2 Usual Dosage in Adults

Initial Dosage:

Tyvaso DPI therapy should begin with one 16 mcg cartridge per treatment session, 4 times daily.

Maintenance Dosage:

Increase dosage by an additional 16 mcg per treatment session at approximately 1- to 2-week intervals. The target maintenance dosage is usually 48 mcg to 64 mcg per session.

If adverse effects preclude titration, continue Tyvaso DPI at the highest tolerated dose.

If a scheduled treatment session is missed, resume therapy as soon as possible at the usual dose.

Dosage for Transition from Tyvaso® (treprostinil) Inhalation Solution:

The following regimens of Tyvaso DPI and Tyvaso give similar exposure:

Tyvaso DPI Cartridge Strength | Tyvaso Number of Breaths
16 mcg | ≤5 (≤30 mcg)
32 mcg | 6 to 7 (36 to 42 mcg)
48 mcg | 8 to 10 (48 to 60 mcg)
64 mcg | 11 to 13 (66 to 78 mcg)
80 mcg | 14 to 15 (84 to 90 mcg)

3 DOSAGE FORMS AND STRENGTHS

Inhalation powder: Single-dose plastic cartridges containing 16 mcg, 32 mcg, 48 mcg, 64 mcg, or 80 mcg of treprostinil as a dry powder formulation.

4 CONTRAINDICATIONS

None.

5 WARNINGS AND PRECAUTIONS

5.1 Risk of Symptomatic Hypotension

Treprostinil is a pulmonary and systemic vasodilator. In patients with low systemic arterial pressure, treatment with Tyvaso DPI may produce symptomatic hypotension.

5.2 Risk of Bleeding

Tyvaso DPI inhibits platelet aggregation and increases the risk of bleeding.

5.3 Effect of Other Drugs on Treprostinil

Co-administration of a cytochrome P450 (CYP) 2C8 enzyme inhibitor (e.g., gemfibrozil) may increase exposure (both Cmax and AUC) to treprostinil. Co-administration of a CYP2C8 enzyme inducer (e.g., rifampin) may decrease exposure to treprostinil. Increased exposure is likely to increase adverse events associated with treprostinil administration, whereas decreased exposure is likely to reduce clinical effectiveness [see Drug Interactions (7.3) and Clinical Pharmacology (12.3)].

5.4 Bronchospasm

Like other inhaled prostaglandins, Tyvaso DPI may cause acute bronchospasm. Patients with asthma or chronic obstructive pulmonary disease (COPD), or other bronchial hyperreactivity, are at increased risk for bronchospasm. Ensure that such patients are treated optimally for reactive airway disease prior to and during treatment with Tyvaso DPI.

6 ADVERSE REACTIONS

The following potential adverse reactions are described in Warnings and Precautions (5):

- Decrease in systemic blood pressure [see Warnings and Precautions (5.1)].
- Bleeding [see Warnings and Precautions (5.2)].

6.1 Clinical Trials Experience

Because clinical trials are conducted under widely varying conditions, adverse reaction rates observed in the clinical trials of a drug cannot be directly compared to rates in the clinical trials of another drug and may not reflect the rates observed in practice.

Pulmonary Arterial Hypertension

Tyvaso DPI

In a 3-week, open-label, single-sequence, safety and tolerability study (BREEZE) conducted in 51 patients on stable doses of Tyvaso Inhalation Solution who switched to a corresponding dose of Tyvaso DPI, the most commonly reported adverse events on Tyvaso DPI during the 3-week treatment phase included cough, headache, dyspnea, and nausea. Patient tolerability, as assessed by incidence of new adverse events following transition to Tyvaso DPI, was consistent with the expected known safety profile of Tyvaso Inhalation Solution. Table 1 lists the adverse events that occurred at a rate of at least 4%.

Table 1: Adverse Events in ≥4% of PAH Patients Receiving Tyvaso DPI in BREEZE (Treatment Phase)
Adverse Event | Tyvaso DPI (n=51) n (%)
Adverse Event | Cough | 18 (35.3)
Headache | 8 (15.7)
Dyspnea | 4 (7.8)
Nausea | 3 (5.9)

The safety of Tyvaso DPI was also studied in an extension phase of the study in which 49 patients were dosed for a duration of 43 patient-years. Fifty-nine percent (59%) of patients achieved a dose of 64 mcg, 4 times daily or higher. The adverse events during this long-term, extension phase were similar to those observed in the 3-week treatment phase.

Tyvaso Inhalation Solution

In a 12-week, placebo-controlled study (TRIUMPH I) of 235 patients with PAH (WHO Group 1 and nearly all NYHA Functional Class III), the most commonly reported adverse reactions on Tyvaso Inhalation Solution included cough and throat irritation, headache, gastrointestinal effects, muscle, jaw or bone pain, dizziness, flushing, and syncope. Table 2 lists the adverse reactions that occurred at a rate of at least 4% and were more frequent in patients treated with Tyvaso Inhalation Solution than with placebo.

Table 2: Adverse Events in ≥4% of PAH Patients Receiving Tyvaso Inhalation Solution and More Frequent [More than 3% greater than placebo] than Placebo in TRIUMPH I
Adverse Event | Treatment n (%)
Adverse Event | Tyvaso Inhalation Solution n=115 | Placebo n=120
Cough | 62 (54) | 35 (29)
Headache | 47 (41) | 27 (23)
Throat Irritation / Pharyngolaryngeal Pain | 29 (25) | 17 (14)
Nausea | 22 (19) | 13 (11)
Flushing | 17 (15) | 1 (<1)
Syncope | 7 (6) | 1 (<1)

Pulmonary Hypertension Associated with ILD

In a 16-week, placebo-controlled study (INCREASE) of 326 patients with PH-ILD (WHO Group 3), adverse reactions on Tyvaso Inhalation Solution were similar to the experience in studies of PAH.

7 DRUG INTERACTIONS

7.1 Bosentan

In a human pharmacokinetic study conducted with bosentan (250 mg/day) and an oral formulation of treprostinil (treprostinil diolamine), no pharmacokinetic interactions between treprostinil and bosentan were observed.

7.2 Sildenafil

In a human pharmacokinetic study conducted with sildenafil (60 mg/day) and an oral formulation of treprostinil (treprostinil diolamine), no pharmacokinetic interactions between treprostinil and sildenafil were observed.

7.3 Effect of Cytochrome P450 Inhibitors and Inducers

In vitro studies of human hepatic microsomes showed that treprostinil does not inhibit cytochrome P450 (CYP) isoenzymes CYP1A2, CYP2A6, CYP2C8, CYP2C9, CYP2C19, CYP2D6, CYP2E1, and CYP3A. Additionally, treprostinil does not induce cytochrome P450 isoenzymes CYP1A2, CYP2B6, CYP2C9, CYP2C19, and CYP3A.

Human pharmacokinetic studies with an oral formulation of treprostinil (treprostinil diolamine) indicated that co-administration of the cytochrome P450 (CYP) 2C8 enzyme inhibitor, gemfibrozil, increases exposure (both Cmax and AUC) to treprostinil. Co-administration of the CYP2C8 enzyme inducer, rifampin, decreases exposure to treprostinil. It is unclear if the safety and efficacy of treprostinil by the inhalation route are altered by inhibitors or inducers of CYP2C8 [see Warnings and Precautions (5.3)].

7.4 Effect of Other Drugs on Treprostinil

Drug interaction studies have been carried out with treprostinil (oral or subcutaneous) co-administered with acetaminophen (4 g/day), warfarin (25 mg/day), and fluconazole (200 mg/day), respectively, in healthy volunteers. These studies did not show a clinically significant effect on the pharmacokinetics of treprostinil. Treprostinil does not affect the pharmacokinetics or pharmacodynamics of warfarin. The pharmacokinetics of R- and S- warfarin and the international normalized ratio (INR) in healthy subjects given a single 25 mg dose of warfarin were unaffected by continuous subcutaneous infusion of treprostinil at an infusion rate of 10 ng/kg/min.

8 USE IN SPECIFIC POPULATIONS

8.1 Pregnancy

Risk Summary

Limited case reports of treprostinil use in pregnant women are insufficient to inform a drug-associated risk of adverse developmental outcomes. However, there are risks to the mother and the fetus associated with pulmonary arterial hypertension (see Clinical Considerations). In animal studies, no adverse reproductive and developmental effects were seen for treprostinil at ≥8 and ≥134 times the human exposure when based on Cmax and AUC, respectively, following a single, inhaled 64 mcg dose of treprostinil inhalation powder.

The estimated background risk of major birth defects and miscarriage for the indicated populations is unknown. All pregnancies have a background risk of birth defect, loss, or other adverse outcomes. In the U.S. general population, the estimated background risk of major birth defects and miscarriage in clinically recognized pregnancies is 2 to 4% and 15 to 20%, respectively.

Clinical Considerations

Disease-associated maternal and embryo-fetal risk

Pulmonary arterial hypertension is associated with an increased risk of maternal and fetal mortality.

Data

Animal reproduction studies have been conducted with treprostinil via continuous subcutaneous administration and with treprostinil diolamine administered orally. In studies with orally administered treprostinil diolamine, no adverse effect doses for fetal viability/growth, fetal development (teratogenicity), and postnatal development were determined in rats. In pregnant rats, no evidence of harm to the fetus was observed following oral administration of treprostinil diolamine at the highest dose tested (20 mg/kg/day), which represents about 129 and 1366 times the human exposure, when based on Cmax and AUC, respectively, following a single, inhaled 64 mcg dose of treprostinil inhalation powder. In pregnant rabbits, external fetal and soft tissue malformations and fetal skeletal malformation occurred. The dose at which no adverse effects were seen (0.5 mg/kg/day) represents about 8 and 134 times the human exposure, when based on Cmax and AUC, respectively, following a single, inhaled 64 mcg dose of treprostinil inhalation powder. No treprostinil treatment-related effects on labor and delivery were seen in animal studies. Animal reproduction studies are not always predictive of human response.

8.2 Lactation

Risk Summary

There are no data on the presence of treprostinil in human milk, the effects on the breastfed infant, or the effects on milk production.

8.4 Pediatric Use

Safety and effectiveness in pediatric patients have not been established. Clinical studies of inhaled treprostinil did not include patients younger than 18 years to determine whether they respond differently from older patients.

8.5 Geriatric Use

Across clinical studies used to establish the effectiveness of Tyvaso Inhalation Solution in patients with PAH and PH-ILD, 268 (47.8%) patients aged 65 years and over were enrolled. The treatment effects and safety profile observed in geriatric patients were similar to younger patients. In general, dose selection for an elderly patient should be cautious, reflecting the greater frequency of hepatic, renal, or cardiac dysfunction, and of concomitant diseases or other drug therapy.

8.6 Patients with Hepatic Insufficiency

Plasma clearance of treprostinil, delivered subcutaneously, was reduced up to 80% in subjects with mild-to-moderate hepatic insufficiency. Uptitrate slowly when treating patients with hepatic insufficiency because of the risk of an increase in systemic exposure which may lead to an increase in dose-dependent adverse effects. Treprostinil has not been studied in patients with severe hepatic insufficiency [see Clinical Pharmacology (12.3)].

8.7 Patients with Renal Impairment

No dose adjustments are required in patients with renal impairment. Treprostinil is not cleared by dialysis [see Clinical Pharmacology (12.3)].

10 OVERDOSAGE

In general, symptoms of overdose with inhaled treprostinil include flushing, headache, hypotension, nausea, vomiting, and diarrhea. Provide general supportive care until the symptoms of overdose have resolved.

11 DESCRIPTION

11.1 Tyvaso DPI Cartridges

Tyvaso DPI consists of single-dose plastic cartridges filled with a white powder containing 1% of treprostinil, a prostacyclin mimetic, which is intended for administration by oral inhalation using the Tyvaso DPI Inhaler only. Treprostinil is adsorbed onto carrier particles consisting of fumaryl diketopiperazine (FDKP). Each cartridge contains 16 mcg, 32 mcg, 48 mcg, 64 mcg, or 80 mcg of treprostinil with approximate fill weights of 1.6 mg, 3.2 mg, 4.8 mg, 6.4 mg, or 8.0 mg of Tyvaso DPI, respectively.

Treprostinil is (1R,2R,3aS,9aS)-[[2,3,3a,4,9,9a-hexahydro-2-hydroxy-1-[(3S)-3-hydroxyoctyl]-1H-benz[f]inden-5-yl]oxy]acetic acid. Treprostinil has a molecular weight of 390.52 and a molecular formula of C23H34O5.

The structural formula of treprostinil is:

12 CLINICAL PHARMACOLOGY

12.1 Mechanism of Action

Treprostinil is a prostacyclin analogue. The major pharmacologic actions of treprostinil are direct vasodilation of pulmonary and systemic arterial vascular beds and inhibition of platelet aggregation.

12.2 Pharmacodynamics

In a clinical trial of 240 healthy volunteers, single doses of Tyvaso Inhalation Solution 54 mcg (the target maintenance dose per session) and 84 mcg (supratherapeutic inhalation dose) prolonged the corrected QTc interval by approximately 10 ms. The QTc effect dissipated as the concentration of treprostinil decreased.

12.3 Pharmacokinetics

Absorption

Treprostinil plasma exposure data were obtained from a 6-treatment, 6-period, 6-sequence, crossover study of Tyvaso DPI and Tyvaso Inhalation Solution in healthy volunteers. The mean Cmax for the 16, 48, and 64 mcg doses of Tyvaso DPI were 0.39, 1.11, and 1.33 ng/mL, respectively, with corresponding median Tmax of 0.17 hr. The mean AUC0-5hr for the 16, 48, and 64 mcg doses of Tyvaso DPI were 0.275, 0.774, and 0.964 hr∙ng/mL, respectively.

Treprostinil systemic exposure (AUC0-5hr and Cmax) of Tyvaso DPI post-inhalation was approximately proportional to the doses administered (16 to 64 mcg).

Distribution

Following parenteral infusion, the steady state volume of distribution (Vss) of treprostinil is approximately 14 L/70 kg ideal body weight.

In vitro treprostinil is 91% bound to human plasma proteins over the 330 to 10,000 mcg/L concentration range.

Elimination

With a single dose of Tyvaso DPI, the mean terminal half-life of treprostinil ranged from 27 to 50 minutes.

Metabolism: Treprostinil is substantially metabolized by the liver, primarily by CYP2C8. Metabolites are excreted in urine (79%) and feces (13%) over 10 days. Five apparently inactive metabolites were detected in the urine, each accounting for 10 to 15% of the dose administered. Four of the metabolites are products of oxidation of the 3-hydroxyloctyl side chain and one is a glucuroconjugated derivative (treprostinil glucuronide).

Excretion: Of subcutaneously administered treprostinil, only 4% is excreted unchanged in urine.

Specific Populations

Hepatic Insufficiency

Plasma clearance of treprostinil, delivered subcutaneously, was reduced up to 80% in subjects presenting with mild-to-moderate hepatic insufficiency. Treprostinil has not been studied in patients with severe hepatic insufficiency [see Use in Specific Populations (8.6)].

Renal Impairment

In patients with severe renal impairment requiring dialysis (n=8), administration of a single 1 mg dose of orally administered treprostinil pre- and post-dialysis resulted in AUC0-inf that was not significantly altered compared to healthy subjects [see Use in Specific Populations (8.7)].

13 NONCLINICAL TOXICOLOGY

13.1 Carcinogenesis, Mutagenesis, Impairment of Fertility

A 2-year rat carcinogenicity study was performed with treprostinil inhalation at target doses of 5.26, 10.6, and 34.1 mcg/kg/day. There was no evidence for carcinogenic potential associated with treprostinil inhalation in rats at systemic exposure levels up to 36 times the clinical exposure at the 64 mcg dose of treprostinil inhalation powder. In vitro and in vivo genetic toxicology studies did not demonstrate any mutagenic or clastogenic effects of treprostinil. Treprostinil sodium did not affect fertility or mating performance of male or female rats given continuous subcutaneous infusions at rates of up to 450 ng treprostinil/kg/min. In this study, males were dosed from 10 weeks prior to mating and through the 2-week mating period. Females were dosed from 2 weeks prior to mating until gestational day 6.

Oral administration of treprostinil diolamine to Tg.rasH2 mice at 0, 5, 10, and 20 mg/kg/day in males and 0, 3, 7.5, and 15 mg/kg/day in females daily for 26 weeks did not significantly increase the incidence of tumors.

Treprostinil diolamine was tested in vivo in a rat micronucleus assay and did not induce an increased incidence of micronucleated polychromatic erythrocytes.

13.2 Animal Toxicology and/or Pharmacology

In a 2-year rat study with treprostinil inhalation solution at target doses of 5.26, 10.6, and 34.1 mcg/kg/day, there were more deaths (11) in the mid- and high-dose treprostinil groups during the first 9 weeks of the study, compared to 1 in control groups. At the high-dose level, males showed a higher incidence of inflammation in teeth and preputial gland, and females showed higher incidences of inflammation and urothelial hyperplasia in the urinary bladder. The exposures in rats at mid- and high-dose levels were about 14 and 36 times, respectively, the clinical exposure at the 64 mcg dose of treprostinil inhalation powder.

14 CLINICAL STUDIES

14.1 Pulmonary Arterial Hypertension (WHO Group 1) (TRIUMPH I)

TRIUMPH I, was a 12-week, randomized, double-blind, placebo-controlled, multicenter study of patients with PAH (NCT00147199). The study population included 235 clinically stable subjects with PAH (WHO Group 1), nearly all with NYHA Class III (98%) symptoms who were receiving either bosentan (an endothelin receptor antagonist) or sildenafil (a phosphodiesterase-5 inhibitor) for at least 3 months prior to study initiation. Concomitant therapy also could have included anticoagulants, other vasodilators (e.g., calcium channel blockers), diuretics, oxygen, and digitalis, but not a prostacyclin. These patients were administered either placebo or Tyvaso Inhalation Solution in 4 daily treatment sessions with a target dose of 9 breaths (54 mcg) per session over the course of the 12-week study. Patients were predominately female (82%), had the origin of PAH as idiopathic/heritable (56%), secondary to connective tissue diseases (33%) or secondary to HIV or previous use of anorexigens (12%); bosentan was the concomitant oral medication in 70% of those enrolled, sildenafil in 30%.

The primary efficacy endpoint of the trial was the change in 6MWD relative to baseline at 12 weeks. 6MWD was measured at peak exposure (between 10 and 60 minutes after dosing), and 3 to 5 hours after bosentan or 0.5 to 2 hours after sildenafil. Patients receiving Tyvaso Inhalation Solution had a placebo-corrected median change from baseline in peak 6MWD of 20 meters at Week 12 (p<0.001). The distribution of these 6MWD changes from baseline at Week 12 were plotted across the range of observed values (Figure 1). 6MWD measured at trough exposure (defined as measurement of 6MWD at least 4 hours after dosing) improved by 14 meters. There were no placebo-controlled 6MWD assessments made after 12 weeks.

Figure 1: Distributions of 6MWD Changes from Baseline at Week 12 During Peak Plasma Concentration of Tyvaso Inhalation Solution

The placebo-corrected median treatment effect on 6MWD was estimated (using the Hodges-Lehmann estimator) within various subpopulations defined by age quartile, gender, geographic region of the study site, disease etiology, baseline 6MWD quartile, and type of background therapy (Figure 2).

Figure 2: Placebo-Corrected Median Treatment Effect (Hodges-Lehmann Estimate with 95% CI) on 6MWD Change from Baseline at Week 12 During Peak Plasma Concentration of Tyvaso Inhalation Solution for Various Subgroups

14.2 Long-term Treatment of PAH

In long-term follow-up of patients who were treated with Tyvaso Inhalation Solution in the pivotal study and the open-label extension (N=206) (NCT00147199), Kaplan-Meier estimates of survival at 1, 2, and 3 years were 97%, 91%, and 82%, respectively. These uncontrolled observations do not allow comparison with a control group not given Tyvaso Inhalation Solution and cannot be used to determine the long-term effect of Tyvaso Inhalation Solution on mortality.

14.3 Pulmonary Hypertension Associated with ILD (WHO Group 3)

INCREASE was a 16-week, randomized, double-blind, placebo-controlled, multicenter study that enrolled 326 patients with PH-ILD (NCT02630316). Enrolled study patients predominately had etiologies of idiopathic interstitial pneumonia (45%) inclusive of idiopathic pulmonary fibrosis, combined pulmonary fibrosis and emphysema (25%), and WHO Group 3 connective tissue disease (22%). The mean baseline 6MWD was 260 meters.

Patients in the INCREASE study were randomized (1:1) to either placebo or Tyvaso Inhalation Solution in 4 daily treatment sessions with a target dose of 9 breaths (54 mcg) per session and a maximum dose of 12 breaths (72 mcg) per session over the course of the 16-week study. Approximately 75% of patients randomized to Tyvaso Inhalation Solution titrated up to a dose of 9 breaths, 4 times daily or greater, with 48% of patients randomized to Tyvaso Inhalation Solution reaching a dose of 12 breaths, 4 times daily during the study.

The primary efficacy endpoint was the change in 6MWD measured at peak exposure (between 10 and 60 minutes after dosing) from baseline to Week 16. Patients receiving Tyvaso Inhalation Solution had a placebo-corrected median change from baseline in peak 6MWD of 21 meters at Week 16 (p=0.004) using Hodges-Lehmann estimate (Figure 3).

Figure 3: Hodges-Lehmann Estimate of Treatment Effect by Visit for 6MWD at Peak Exposure of Tyvaso Inhalation Solution (PH-ILD)

The treatment effect on 6MWD at Week 16 was consistent for various subgroups, including etiology of PH-ILD, disease severity, age, sex, baseline hemodynamics, and dose (Figure 4).

Figure 4: Forest Plot on Subgroup Analyses of Peak 6MWD (Meter) at Week 16 (PH-ILD)

Time to clinical worsening in the INCREASE study was defined as the time of randomization until 1 of the following criteria were met: hospitalization due to a cardiopulmonary indication, decrease in 6MWD >15% from baseline directly related to PH-ILD at 2 consecutive visits and at least 24 hours apart, death (all causes), or lung transplantation. Treatment with Tyvaso Inhalation Solution in patients with PH-ILD resulted in numerically fewer hospitalizations. The numbers of reported deaths were the same for both treatment groups (Table 3). Overall, treatment with Tyvaso Inhalation Solution demonstrated a statistically significant increase in the time to first clinical worsening event (log-rank test p=0.041; Figure 5), and a 39% overall reduction in the risk of a clinical worsening event (HR=0.61 [95% CI; 0.40, 0.92]; Figure 5).

Table 3: Clinical Worsening Events (PH-ILD)
 |  | Tyvaso Inhalation Solution n=163 n (%) | Placebo n=163 n (%) | HR (95% CI)
Clinical worsening |  | 37 (22.7%) | 54 (33.1%) | 0.61 (0.40, 0.92)
First contributing event | Hospitalization due to a cardiopulmonary indication | 18 (11.0%) | 24 (14.7%)
First contributing event | Decrease in 6MWD >15% from baseline directly related to PH-ILD | 13 (8.0%) | 26 (16.0%)
First contributing event | Death (all causes) | 4 (2.5%) | 4 (2.5%)
First contributing event | Lung transplantation | 2 (1.2%) | 0
First of each event | Hospitalization due to a cardiopulmonary indication | 21 (12.9%) | 30 (18.4%)
First of each event | Decrease in 6MWD >15% from baseline directly related to PH-ILD | 16 (9.8%) | 31 (19.0%)
First of each event | Death (all causes) | 8 (4.9%) | 10 (6.1%)
First of each event | Lung transplantation | 2 (1.2%) | 1 (0.6%)

Figure 5: Kaplan-Meier Plot of Time to Clinical Worsening Events (PH-ILD)

16 HOW SUPPLIED/STORAGE AND HANDLING

Tyvaso DPI (treprostinil) inhalation powder is available as 16 mcg, 32 mcg, 48 mcg, 64 mcg, or 80 mcg of treprostinil in single-dose plastic cartridges with approximate fill weights of 1.6 mg, 3.2 mg, 4.8 mg, 6.4 mg, or 8.0 mg of Tyvaso DPI, respectively. Four cartridges are contained in a single cavity of a blister strip. A card contains 7 blister strips separated by perforations for a total of 28 cartridges of each labeled strength in Titration and Maintenance Kits. For convenience, the perforation allows users to remove a single blister strip containing 4 cartridges. The Institutional Kits contain 4 blister strips for a total of 16 cartridges of each labeled strength.

The cartridges are color-coded, purple for 16 mcg, dark blue for 32 mcg, light blue for 48 mcg, light green for 64 mcg, and orange for 80 mcg. Each cartridge is marked with "Tyvaso DPI" and the corresponding dosage strength of "16 mcg", "32 mcg", "48 mcg", "64 mcg", or "80 mcg".

The Tyvaso DPI Inhaler is individually packaged in a clear overwrap. The inhaler is fully assembled with a removable mouthpiece cover. The Tyvaso DPI Inhaler can be used for up to 7 days from the date of first use. After 7 days of use, the inhaler must be discarded and replaced with a new inhaler.

Tyvaso DPI is available in the following configurations:

 |  | Kit Contents
Description | NDC | Number of Cartridges and Strength | Number of Inhalers
Tyvaso DPI (treprostinil) Inhalation Powder Titration Kit | 66302-600-02 | 112 cartridges, each containing 16 mcg per cartridge | 5
Tyvaso DPI (treprostinil) Inhalation Powder Titration Kit | 66302-600-02 | 84 cartridges, each containing 32 mcg per cartridge | 5
Tyvaso DPI (treprostinil) Inhalation Powder Titration Kit | 66302-610-02 | 112 cartridges, each containing 16 mcg per cartridge | 5
Tyvaso DPI (treprostinil) Inhalation Powder Titration Kit | 66302-610-02 | 112 cartridges, each containing 32 mcg per cartridge | 5
Tyvaso DPI (treprostinil) Inhalation Powder Titration Kit | 66302-610-02 | 28 cartridges, each containing 48 mcg per cartridge | 5
Tyvaso DPI (treprostinil) Inhalation Powder Maintenance Kit | 66302-616-03 | 112 cartridges, each containing 16 mcg per cartridge | 5
Tyvaso DPI (treprostinil) Inhalation Powder Maintenance Kit | 66302-632-03 | 112 cartridges, each containing 32 mcg per cartridge | 5
Tyvaso DPI (treprostinil) Inhalation Powder Maintenance Kit | 66302-648-03 | 112 cartridges, each containing 48 mcg per cartridge | 5
Tyvaso DPI (treprostinil) Inhalation Powder Maintenance Kit | 66302-664-03 | 112 cartridges, each containing 64 mcg per cartridge | 5
Tyvaso DPI (treprostinil) Inhalation Powder Maintenance Kit | 66302-680-03 | 112 cartridges, each containing 80 mcg per cartridge | 5
Tyvaso DPI (treprostinil) Inhalation Powder Maintenance Kit | 66302-620-03 | 112 cartridges, each containing 32 mcg per cartridge | 5
Tyvaso DPI (treprostinil) Inhalation Powder Maintenance Kit | 66302-620-03 | 112 cartridges, each containing 48 mcg per cartridge | 5
Tyvaso DPI (treprostinil) Inhalation Powder Maintenance Kit | 66302-630-03 | 112 cartridges, each containing 32 mcg per cartridge | 5
Tyvaso DPI (treprostinil) Inhalation Powder Maintenance Kit | 66302-630-03 | 112 cartridges, each containing 64 mcg per cartridge | 5
Tyvaso DPI (treprostinil) Inhalation Powder Maintenance Kit | 66302-640-03 | 112 cartridges, each containing 48 mcg per cartridge | 5
Tyvaso DPI (treprostinil) Inhalation Powder Maintenance Kit | 66302-640-03 | 112 cartridges, each containing 64 mcg per cartridge | 5
Tyvaso DPI (treprostinil) Inhalation Powder Maintenance Kit | 66302-650-03 | 112 cartridges, each containing 16 mcg per cartridge | 5
Tyvaso DPI (treprostinil) Inhalation Powder Maintenance Kit | 66302-650-03 | 112 cartridges, each containing 48 mcg per cartridge | 5
Tyvaso DPI (treprostinil) Inhalation Powder Maintenance Kit | 66302-650-03 | 112 cartridges, each containing 64 mcg per cartridge | 5
Tyvaso DPI (treprostinil) Inhalation Powder Maintenance Kit | 66302-660-03 | 112 cartridges, each containing 48 mcg per cartridge | 5
Tyvaso DPI (treprostinil) Inhalation Powder Maintenance Kit | 66302-660-03 | 112 cartridges, each containing 80 mcg per cartridge | 5
Tyvaso DPI (treprostinil) Inhalation Powder Maintenance Kit | 66302-670-03 | 112 cartridges, each containing 64 mcg per cartridge | 5
Tyvaso DPI (treprostinil) Inhalation Powder Maintenance Kit | 66302-670-03 | 112 cartridges, each containing 80 mcg per cartridge | 5
Tyvaso DPI (treprostinil) Inhalation Powder Institutional Kit | 66302-716-04 | 16 cartridges, each containing 16 mcg per cartridge | 2
Tyvaso DPI (treprostinil) Inhalation Powder Institutional Kit | 66302-732-04 | 16 cartridges, each containing 32 mcg per cartridge | 2
Tyvaso DPI (treprostinil) Inhalation Powder Institutional Kit | 66302-748-04 | 16 cartridges, each containing 48 mcg per cartridge | 2
Tyvaso DPI (treprostinil) Inhalation Powder Institutional Kit | 66302-764-04 | 16 cartridges, each containing 64 mcg per cartridge | 2
Tyvaso DPI (treprostinil) Inhalation Powder Institutional Kit | 66302-780-04 | 16 cartridges, each containing 80 mcg per cartridge | 2
Tyvaso DPI (treprostinil) Inhalation Powder Institutional Kit | 66302-720-04 | 16 cartridges, each containing 32 mcg per cartridge | 2
Tyvaso DPI (treprostinil) Inhalation Powder Institutional Kit | 66302-720-04 | 16 cartridges, each containing 48 mcg per cartridge | 2

Blister Storage:

Storage
Tyvaso DPI Presentation | Refrigerated storage 2°C to 8°C (36°F to 46°F) | Room temperature storage 20°C to 25°C (68°F to 77°F), excursions permitted 15°C to 30°C (59°F to 86°F)
Sealed (Unopened) Blister Cards or Strips | May be stored until the expiration date printed on the blisters. | Must be used within 8 weeks.
Opened Blister Strips | Do not put a blister card or strip back into the refrigerator after being opened or stored at room temperature. | Must be used within 3 days.

Inhaler Storage:

Store at 2°C to 25°C (36°F to 77°F); excursions permitted. The Tyvaso DPI Inhaler may be stored refrigerated but should be at room temperature for 10 minutes before use. The inhaler can be used for up to 7 days from the date of first use. After 7 days of use, the inhaler must be discarded and replaced with a new inhaler.

Handling:

If refrigerated, cartridges and inhaler should be at room temperature for 10 minutes before use.

17 PATIENT COUNSELING INFORMATION

Advise the patient to read the FDA-approved patient labeling (Instructions for Use).

Train patients in the administration process for Tyvaso DPI, including dosing, Tyvaso DPI Inhaler setup, operation, cleaning, and maintenance, according to the instructions for use [see Dosage and Administration (2.1, 2.2)].

Advise patients that after 7 days of use, the inhaler must be discarded and replaced with a new inhaler [see Dosage and Administration (2.1)].

Instruct patients to use Tyvaso DPI only with the Tyvaso DPI Inhaler [see Dosage and Administration (2.1)].

If a scheduled treatment session is missed, resume therapy as soon as possible [see Dosage and Administration (2.2)].

©Copyright 2025 United Therapeutics Corp. All rights reserved.
Tyvaso DPI® and Tyvaso® are registered trademarks of United Therapeutics Corporation.

Tyvaso DPI manufactured by:

MannKind Corporation
Danbury, CT 06810

Tyvaso DPI manufactured for and distributed by:

United Therapeutics Corp.
Research Triangle Park, NC 27709

Instructions
for Use

TYVASO [ tī-vā'-sō ] DPI®
(treprostinil) Inhalation Powder
For oral inhalation only

Table of Contents
 | page(s)
Read Before Starting | 1
Important Information | 2
Storing TYVASO DPI Inhalers and Cartridges | 3
Preparing to Inhale TYVASO DPI | 4-7
Inhaling TYVASO DPI | 8-9
Removing the Used Cartridge | 10
Disposing of TYVASO DPI Cartridge | 11
Inhaling Multiple Cartridges of TYVASO DPI | 12
Caring for Your TYVASO DPI Inhaler | 13
Disposing of Your TYVASO DPI Inhaler | 13

Read Before Starting

 | Parts of the TYVASO DPI Inhaler (see Figure A) | Your Starter Kit includes a Carrying Case (see Figure B) | TYVASO DPI Blister Cards (see Figure C)
This Instructions for Use contains information on how to inhale TYVASO DPI (treprostinil) Inhalation Powder. Read this Instructions for Use carefully before you start using your inhaler and each time you get a new inhaler. There may be new information. This information does not take the place of talking to your healthcare provider about your medical condition or your treatment. Your healthcare provider should show you how to use your inhaler the right way before you use it for the first time. | Figure A | The TYVASO DPI inhaler and blister strips can be stored in the carrying case when using outside of your home or traveling. | Figure C
This Instructions for Use contains information on how to inhale TYVASO DPI (treprostinil) Inhalation Powder. Read this Instructions for Use carefully before you start using your inhaler and each time you get a new inhaler. There may be new information. This information does not take the place of talking to your healthcare provider about your medical condition or your treatment. Your healthcare provider should show you how to use your inhaler the right way before you use it for the first time. | Figure A | Figure B | Figure C

Important Information

Important information you need to know before inhaling TYVASO DPI Inhalation Powder using the TYVASO DPI Inhaler | - Take TYVASO DPI exactly as prescribed by your healthcare provider. - Take TYVASO DPI 4 times per day while you are awake, about 4 hours apart. - If you miss a dose, take it as soon as possible at your usual dose. - If your prescribed dose is higher than 80 mcg per treatment session, you will need to use more than 1 cartridge. If using more than 1 cartridge, the cartridges can be used in any order, regardless of cartridge strength. - If you need to use more than 1 cartridge for your dose, remove the used cartridge from the inhaler before getting a new one. You can tell a cartridge has been used when the cartridge cup has moved from the front to the middle position in the cartridge base. - Only TYVASO DPI cartridges should be used with the TYVASO DPI Inhaler. - Each cartridge is for 1 time (single use) only. Use a new cartridge for each treatment session. After each treatment session, throw away the used cartridge right away. - Do not open the cartridges. The inhaler opens the cartridge automatically during use. - Warning: If any powder from the cartridge spills on your hands, throw away the cartridge right away into regular household trash and wash your hands. Then start with a new cartridge. - Do not breathe in the TYVASO DPI treprostinil powder in any other way. - Do not put cartridges in your mouth. - Do not swallow cartridges. - Use only 1 inhaler at a time. The same inhaler should be used even when needing to use more than 1 cartridge for your dose. Inhale 1 cartridge at a time. - The inhaler lasts for 7 days. After 7 days of use, throw away your used inhaler and get a new one. - Store the inhaler in a clean, dry place with the mouthpiece cover on until your next dose.
TYVASO DPI cartridges come in 5 strengths (see Figure D). Important: Always make sure you have the right number of TYVASO DPI cartridges for your dose before you start. Only use TYVASO DPI cartridges with the TYVASO DPI Inhaler. | - Take TYVASO DPI exactly as prescribed by your healthcare provider. - Take TYVASO DPI 4 times per day while you are awake, about 4 hours apart. - If you miss a dose, take it as soon as possible at your usual dose. - If your prescribed dose is higher than 80 mcg per treatment session, you will need to use more than 1 cartridge. If using more than 1 cartridge, the cartridges can be used in any order, regardless of cartridge strength. - If you need to use more than 1 cartridge for your dose, remove the used cartridge from the inhaler before getting a new one. You can tell a cartridge has been used when the cartridge cup has moved from the front to the middle position in the cartridge base. - Only TYVASO DPI cartridges should be used with the TYVASO DPI Inhaler. - Each cartridge is for 1 time (single use) only. Use a new cartridge for each treatment session. After each treatment session, throw away the used cartridge right away. - Do not open the cartridges. The inhaler opens the cartridge automatically during use. - Warning: If any powder from the cartridge spills on your hands, throw away the cartridge right away into regular household trash and wash your hands. Then start with a new cartridge. - Do not breathe in the TYVASO DPI treprostinil powder in any other way. - Do not put cartridges in your mouth. - Do not swallow cartridges. - Use only 1 inhaler at a time. The same inhaler should be used even when needing to use more than 1 cartridge for your dose. Inhale 1 cartridge at a time. - The inhaler lasts for 7 days. After 7 days of use, throw away your used inhaler and get a new one. - Store the inhaler in a clean, dry place with the mouthpiece cover on until your next dose.
Figure D | - Take TYVASO DPI exactly as prescribed by your healthcare provider. - Take TYVASO DPI 4 times per day while you are awake, about 4 hours apart. - If you miss a dose, take it as soon as possible at your usual dose. - If your prescribed dose is higher than 80 mcg per treatment session, you will need to use more than 1 cartridge. If using more than 1 cartridge, the cartridges can be used in any order, regardless of cartridge strength. - If you need to use more than 1 cartridge for your dose, remove the used cartridge from the inhaler before getting a new one. You can tell a cartridge has been used when the cartridge cup has moved from the front to the middle position in the cartridge base. - Only TYVASO DPI cartridges should be used with the TYVASO DPI Inhaler. - Each cartridge is for 1 time (single use) only. Use a new cartridge for each treatment session. After each treatment session, throw away the used cartridge right away. - Do not open the cartridges. The inhaler opens the cartridge automatically during use. - Warning: If any powder from the cartridge spills on your hands, throw away the cartridge right away into regular household trash and wash your hands. Then start with a new cartridge. - Do not breathe in the TYVASO DPI treprostinil powder in any other way. - Do not put cartridges in your mouth. - Do not swallow cartridges. - Use only 1 inhaler at a time. The same inhaler should be used even when needing to use more than 1 cartridge for your dose. Inhale 1 cartridge at a time. - The inhaler lasts for 7 days. After 7 days of use, throw away your used inhaler and get a new one. - Store the inhaler in a clean, dry place with the mouthpiece cover on until your next dose.
If you are having problems with your TYVASO DPI Inhaler, have any side effects, or if your TYVASO DPI Inhaler breaks and you need a new one, please call 1-844-UNITHER (1-844-864-8437). | - Take TYVASO DPI exactly as prescribed by your healthcare provider. - Take TYVASO DPI 4 times per day while you are awake, about 4 hours apart. - If you miss a dose, take it as soon as possible at your usual dose. - If your prescribed dose is higher than 80 mcg per treatment session, you will need to use more than 1 cartridge. If using more than 1 cartridge, the cartridges can be used in any order, regardless of cartridge strength. - If you need to use more than 1 cartridge for your dose, remove the used cartridge from the inhaler before getting a new one. You can tell a cartridge has been used when the cartridge cup has moved from the front to the middle position in the cartridge base. - Only TYVASO DPI cartridges should be used with the TYVASO DPI Inhaler. - Each cartridge is for 1 time (single use) only. Use a new cartridge for each treatment session. After each treatment session, throw away the used cartridge right away. - Do not open the cartridges. The inhaler opens the cartridge automatically during use. - Warning: If any powder from the cartridge spills on your hands, throw away the cartridge right away into regular household trash and wash your hands. Then start with a new cartridge. - Do not breathe in the TYVASO DPI treprostinil powder in any other way. - Do not put cartridges in your mouth. - Do not swallow cartridges. - Use only 1 inhaler at a time. The same inhaler should be used even when needing to use more than 1 cartridge for your dose. Inhale 1 cartridge at a time. - The inhaler lasts for 7 days. After 7 days of use, throw away your used inhaler and get a new one. - Store the inhaler in a clean, dry place with the mouthpiece cover on until your next dose.

Storing TYVASO DPI Inhalers and Cartridges

Storing TYVASO DPI Inhalers | Storing Unopened Blister Cards and Strips |  |  |  | Storing Opened Blister Strips
Store TYVASO DPI Inhalers, with the mouthpiece on, in a clean, dry place at room temperature between 68°F to 77°F (20°C to 25°C), such as a drawer or medicine cabinet (see Figure E). Inhalers may be stored in the refrigerator between 36°F to 46°F (2°C to 8°C), but should be left out at room temperature for 10 minutes before use. | Store unopened blister cards and strips in a clean, dry place at room temperature, such as a drawer or medicine cabinet. You can store in the carrying case when using outside your home or traveling (see Figure F).; Do not use after 8 weeks if stored at room temperature.; Unopened blister cards and strips may also be stored in the refrigerator (see Figure G). |  |  | Figure F | Store opened blister strips in a clean, dry place at room temperature (see Figure H), such as a drawer or medicine cabinet. Opened blister strips must be used within 3 days.; Do not put a blister strip back into the refrigerator after being opened or stored at room temperature.
Do not leave or store cartridges in the inhaler. Keep out of the reach of children. | Do not use after the Expiration Date has passed. |  |  |  | Figure H
Figure E |  | Important: If refrigerated, cartridges and inhaler should be left out at room temperature for 10 minutes before use. |  | Figure G | Figure H
Figure E |  | ROOM TEMPERATURE | 10 mins. | Figure G | Figure H

Preparing to Inhale TYVASO DPI

Step 1 : Select the TYVASO DPI cartridges for your dose (see Figure I) |  |  |  |  | Step 2 : Tear off 1 strip |  | Step 3 : Check the expiration date on the strip
Select the TYVASO DPI cartridges for your dose (see Figure I).; Note: If using more than 1 cartridge, the cartridges can be used in any order, regardless of cartridge strength. |  |  |  |  | Tear along the perforation to remove 1 strip from the blister card (see Figure J). | Figure J | Check the expiration date on the foil strip label (see Figure K).; Do not use the cartridges if the Expiration Date on the strip has passed.
If your prescribed TYVASO DPI dose is 16 mcg, use... | If your prescribed TYVASO DPI dose is 32 mcg, use... | If your prescribed TYVASO DPI dose is 48 mcg, use... | If your prescribed TYVASO DPI dose is 64 mcg, use... | If your prescribed TYVASO DPI dose is 80 mcg, use... | Tear along the perforation to remove 1 strip from the blister card (see Figure J). | Figure J | Figure K
If your prescribed TYVASO DPI dose is more than 80 mcg per treatment session, you will need to use more than 1 cartridge to get the right dose. Example: If your prescribed TYVASO DPI dose is 96 mcg per treatment session, you can use... |  |  |  |  | Tear along the perforation to remove 1 strip from the blister card (see Figure J). | Figure J | Figure K
Figure I |  |  |  |  | Tear along the perforation to remove 1 strip from the blister card (see Figure J). | Figure J | Figure K

Step 4 : Remove cartridge(s) from strip |  |  |  |  | Step 5 : Check supplies before continuing
- Remove cartridge(s) from the strip by pushing on the white plastic to push the cartridge out (see Figure L). Note: Pushing on the cup will not damage the cartridge. - Make sure to remove the right number of cartridges for your dose. - After you have removed a cartridge (or cartridges) from the strip, if any unused cartridges remain in the strip, store the strip at room temperature. Do not put a blister strip back into the refrigerator after being opened. |  |  |  |  |  | Check that you have the right cartridge(s) for your dose.
- Remove cartridge(s) from the strip by pushing on the white plastic to push the cartridge out (see Figure L). Note: Pushing on the cup will not damage the cartridge. - Make sure to remove the right number of cartridges for your dose. - After you have removed a cartridge (or cartridges) from the strip, if any unused cartridges remain in the strip, store the strip at room temperature. Do not put a blister strip back into the refrigerator after being opened. |  |  |  |  |  | Only use one inhaler for multiple cartridges. Your inhaler lasts for 7 days.
Figure L
 | Important: If refrigerated, cartridges and inhaler should be left out at room temperature for 10 minutes before use. | ROOM TEMPERATURE | 10 mins.

Step 6: Load a cartridge
Place Inhaler on Flat Surface Place the inhaler on a flat surface (see Figure M). | Open Inhaler Open the inhaler by lifting the mouthpiece to an upright (vertical) position (see Figure N). Important: If the cartridge came from a strip stored in the refrigerator (or if you stored the inhaler in the refrigerator), leave the cartridge and inhaler at room temperature for 10 minutes to remove condensation. | Place Cartridge in Inhaler; - Hold the cartridge with the cup facing down (see Figure O). - Line up the cartridge with the opening in the inhaler. The pointed end of the cartridge should line up with the pointed end in the inhaler (see Figure P). - Place the cartridge into the inhaler so that it lies flat.
Figure M | Open Inhaler Open the inhaler by lifting the mouthpiece to an upright (vertical) position (see Figure N). Important: If the cartridge came from a strip stored in the refrigerator (or if you stored the inhaler in the refrigerator), leave the cartridge and inhaler at room temperature for 10 minutes to remove condensation. | Place Cartridge in Inhaler; - Hold the cartridge with the cup facing down (see Figure O). - Line up the cartridge with the opening in the inhaler. The pointed end of the cartridge should line up with the pointed end in the inhaler (see Figure P). - Place the cartridge into the inhaler so that it lies flat.
 | Figure N | Figure O | Figure P

Close Inhaler Close the inhaler (this will open the cartridge). You should feel a snap when the inhaler is closed (see Figure Q). Important: Now that the cartridge is loaded, keep the inhaler level to avoid loss of the TYVASO DPI powder, until it is in your mouth (see Figure R). |  | Not keeping the inhaler level could cause a loss of TYVASO DPI powder (see Figure S)
Close Inhaler Close the inhaler (this will open the cartridge). You should feel a snap when the inhaler is closed (see Figure Q). Important: Now that the cartridge is loaded, keep the inhaler level to avoid loss of the TYVASO DPI powder, until it is in your mouth (see Figure R). |  | If any powder from the cartridge spills:; - Wash your hands right away if the powder comes into contact with your hands, - Throw away the cartridge into household trash, and - Repeat Steps 4, 5, and 6 to load a new cartridge
Figure Q | Figure R | DO NOT turn inhaler upside down. | DO NOT point the mouthpiece down. | DO NOT shake or drop the inhaler.
Figure Q | Figure R | This can cause a loss of TYVASO DPI powder.
Figure Q | Figure R | Figure S

Inhaling TYVASO DPI

Before inhaling TYVASO DPI, fully review all parts of Step 7 before you take your dose.

Step 7: Inhale Your Dose

Remove the Mouthpiece Cover (see Figure T).
Important: Keep the inhaler level during and after removal of the blue mouthpiece cover to prevent loss of TYVASO DPI powder.

Hold Inhaler Near Cheek
While keeping the inhaler level, carefully pick up the inhaler and bring it near your cheek, but not in front of your mouth (see Figure U).

Exhale
Holding the inhaler away from your mouth, fully blow out (exhale) (see Figure V).

Figure T

Figure U

Figure V

Position Inhaler in Mouth

- Keeping your head level, place the mouthpiece in your mouth and close your lips around the mouthpiece to form a seal.
- Tilt the inhaler slightly downward while keeping your head level (see Figure W).
  Note: This helps prevent the powder from being blocked by your tongue.

Inhale Deeply, Hold Breath, then Exhale

- With your mouth closed around the mouthpiece, inhale deeply through the inhaler (see Figure X).
- Then remove the inhaler from your mouth and hold your breath for as long as you comfortably can (see Figure Y).
- Then blow out (exhale) and continue to breathe normally (see Figure Z).

Figure W

Figure X

Figure Y

Figure Z

Removing the Used Cartridge

Step 8 : Remove the used cartridge
Replace Mouthpiece Cover Place the mouthpiece cover back onto the inhaler (see Figure AA).; Note: This keeps your fingers off the exposed mouthpiece. | Open Inhaler Open the inhaler by lifting up the mouthpiece to an upright (vertical) position (see Figure AB). | Remove Cartridge; - Remove the used cartridge from the blue base (see Figure AC). - The cup should now be in the middle of the used cartridge (see Figure AD). Warning: If any powder from the cartridge spills on your hands, wash your hands right away.
Figure AA | Figure AB | Figure AC
Figure AA | Figure AB | Figure AC | The cup moves to the middle of the cartridge when it has been used.
Figure AA | Figure AB | Figure AC | Figure AD

Disposing of TYVASO DPI Cartridges

Step 9 : Throw away used cartridge

Throw away the used cartridge in your regular household trash (see Figure AE).

Figure AE

Inhaling Multiple Cartridges of TYVASO DPI

Step 10 : Inhaling multiple cartridges (skip if not needed)

If your dose requires you to inhale multiple cartridges, repeat steps 6 through 9 for each cartridge.

Warning: Be careful not to mix NEW cartridges with used cartridges (see Figure AG).

Example: If your prescribed TYVASO DPI dose is 96 mcg per treatment session, you can use one 32 mcg cartridge and one 64 mcg cartridge (see Figure AF):

The cup moves to the middle of the cartridge when it has been used.

Figure AF

Figure AG

Caring for Your TYVASO DPI Inhaler |  | Disposing of Your TYVASO DPI Inhaler
Inhaler Care Instructions |  | Throw away used inhaler after 7 days of use
Cleaning After taking your dose, powder residue in the mouthpiece is normal; this will not affect your dose. | Use Time Only use 1 inhaler at a time. The same inhaler can be used to take 16 mcg, 32 mcg, 48 mcg, 64 mcg, or 80 mcg cartridges. | After 7 days of use, throw away the used inhaler in your regular household trash (see Figure AH and Figure AI).
The outside of the inhaler can be wiped with a clean, dry cloth only, if needed. Never wash the inhaler. Always keep the inhaler dry. | Replace the inhaler after 7 days (see Figure AH and Figure AI). Keep track of 7 days from when you start using the inhaler with a calendar. | Figure AI
 | Figure AH | Figure AI

For further questions and information, or to report a problem with your device or any side effects with your TYVASO DPI, please call 1-844-UNITHER (1-844-864-8437).

This Instructions for Use has been approved by the U.S. Food and Drug Administration.
Revised: October 2024

TYVASO DPI® is a registered trademark of United Therapeutics Corporation.

Patents: www.tyvasodpi.com/patent

Distributed by:
United Therapeutics Corporation
Research Triangle Park, NC 27709
USA

Manufactured by:
MannKind Corporation
Danbury, CT 06810
USA

10/2024
30-1311-006-03

PRINCIPAL DISPLAY PANEL - 16 mcg Maintenance Kit

NDC 66302-616-03
Rx ONLY

Maintenance Kit

FOR ORAL INHALATION ONLY
KIT CONTAINS:

112 cartridges, each containing
16 mcg per cartridge
+ 5
Inhalers

This MAINTENANCE KIT is NOT intended
for initial titration.

TYVASO DPI®
(treprostinil)
INHALATION
POWDER

16
mcg per
cartridge

BLISTER STORAGE
Unopened Blister Cards/Strips:
Store refrigerated at 2°C to 8°C (36°F to 46°F). Discard
unopened blister strips stored at room temperature after 8 weeks.

Opened Blister Strips:
Store at 20°C to 25°C (68°F to 77°F) with excursions permitted
to 15°C to 30°C (59°F to 86°F) [See USP Controlled Room
Temperature]. Discard opened blister strips holding unused
cartridges 3 days after opening.

INHALER STORAGE
Store at 2°C to 25°C (36°F to 77°F) excursions permitted.
May be stored refrigerated, but must be at room temperature
before use.

The inhaler can be used for up to 7 days from the date of
first use. After 7 days of use, discard the used inhaler and
replace with a new inhaler.

PRINCIPAL DISPLAY PANEL - 16 mcg Institutional Kit

NDC 66302-716-04
Rx ONLY

Institutional Kit

FOR ORAL INHALATION ONLY
KIT CONTAINS:

16 cartridges, each containing
16 mcg per cartridge
+ 2
Inhalers

This INSTITUTIONAL KIT is NOT intended
for initial titration.

TYVASO DPI®
(treprostinil)
INHALATION
POWDER

16
mcg per
cartridge

BLISTER STORAGE
Unopened Blister Cards/Strips:
Store refrigerated at 2°C to 8°C (36°F to 46°F). Discard
unopened blister strips stored at room temperature after 8 weeks.

Opened Blister Strips:
Store at 20°C to 25°C (68°F to 77°F) with excursions permitted
to 15°C to 30°C (59°F to 86°F) [See USP Controlled Room
Temperature]. Discard opened blister strips holding unused
cartridges 3 days after opening.

INHALER STORAGE
Store at 2°C to 25°C (36°F to 77°F) excursions permitted.
May be stored refrigerated, but must be at room temperature
before use.

The inhaler can be used for up to 7 days from the date of
first use. After 7 days of use, discard the used inhaler and
replace with a new inhaler.

PRINCIPAL DISPLAY PANEL - 32 mcg Maintenance Kit

NDC 66302-632-03
Rx ONLY

Maintenance Kit

FOR ORAL INHALATION ONLY
KIT CONTAINS:

112 cartridges, each containing
32 mcg per cartridge
+ 5
Inhalers

This MAINTENANCE KIT is NOT intended
for initial titration.

TYVASO DPI®
(treprostinil)
INHALATION
POWDER

32
mcg per
cartridge

BLISTER STORAGE
Unopened Blister Cards/Strips:
Store refrigerated at 2°C to 8°C (36°F to 46°F). Discard
unopened blister strips stored at room temperature after 8 weeks.

Opened Blister Strips:
Store at 20°C to 25°C (68°F to 77°F) with excursions permitted
to 15°C to 30°C (59°F to 86°F) [See USP Controlled Room
Temperature]. Discard opened blister strips holding unused
cartridges 3 days after opening.

INHALER STORAGE
Store at 2°C to 25°C (36°F to 77°F) excursions permitted.
May be stored refrigerated, but must be at room temperature
before use.

The inhaler can be used for up to 7 days from the date of
first use. After 7 days of use, discard the used inhaler and
replace with a new inhaler.

PRINCIPAL DISPLAY PANEL - 32 mcg Institutional Kit

NDC 66302-732-04
Rx ONLY

Institutional Kit

FOR ORAL INHALATION ONLY
KIT CONTAINS:

16 cartridges, each containing
32 mcg per cartridge
+ 2
Inhalers

This INSTITUTIONAL KIT is NOT intended
for initial titration.

TYVASO DPI®
(treprostinil)
INHALATION
POWDER

32
mcg per
cartridge

BLISTER STORAGE
Unopened Blister Cards/Strips:
Store refrigerated at 2°C to 8°C (36°F to 46°F). Discard
unopened blister strips stored at room temperature after 8 weeks.

Opened Blister Strips:
Store at 20°C to 25°C (68°F to 77°F) with excursions permitted
to 15°C to 30°C (59°F to 86°F) [See USP Controlled Room
Temperature]. Discard opened blister strips holding unused
cartridges 3 days after opening.

INHALER STORAGE
Store at 2°C to 25°C (36°F to 77°F) excursions permitted.
May be stored refrigerated, but must be at room temperature
before use.

The inhaler can be used for up to 7 days from the date of
first use. After 7 days of use, discard the used inhaler and
replace with a new inhaler.

PRINCIPAL DISPLAY PANEL - 48 mcg Maintenance Kit

NDC 66302-648-03
Rx ONLY

Maintenance Kit

FOR ORAL INHALATION ONLY
KIT CONTAINS:

112 cartridges, each containing
48 mcg per cartridge
+ 5
Inhalers

This MAINTENANCE KIT is NOT intended
for initial titration.

TYVASO DPI®
(treprostinil)
INHALATION
POWDER

48
mcg per
cartridge

BLISTER STORAGE
Unopened Blister Cards/Strips:
Store refrigerated at 2°C to 8°C (36°F to 46°F). Discard
unopened blister strips stored at room temperature after 8 weeks.

Opened Blister Strips:
Store at 20°C to 25°C (68°F to 77°F) with excursions permitted
to 15°C to 30°C (59°F to 86°F) [See USP Controlled Room
Temperature]. Discard opened blister strips holding unused
cartridges 3 days after opening.

INHALER STORAGE
Store at 2°C to 25°C (36°F to 77°F) excursions permitted.
May be stored refrigerated, but must be at room temperature
before use.

The inhaler can be used for up to 7 days from the date of
first use. After 7 days of use, discard the used inhaler and
replace with a new inhaler.

PRINCIPAL DISPLAY PANEL - 48 mcg Institutional Kit

NDC 66302-748-04
Rx ONLY

Institutional Kit

FOR ORAL INHALATION ONLY
KIT CONTAINS:

16 cartridges, each containing
48 mcg per cartridge
+ 2
Inhalers

This INSTITUTIONAL KIT is NOT intended
for initial titration.

TYVASO DPI®
(treprostinil)
INHALATION
POWDER

48
mcg per
cartridge

BLISTER STORAGE
Unopened Blister Cards/Strips:
Store refrigerated at 2°C to 8°C (36°F to 46°F). Discard
unopened blister strips stored at room temperature after 8 weeks.

Opened Blister Strips:
Store at 20°C to 25°C (68°F to 77°F) with excursions permitted
to 15°C to 30°C (59°F to 86°F) [See USP Controlled Room
Temperature]. Discard opened blister strips holding unused
cartridges 3 days after opening.

INHALER STORAGE
Store at 2°C to 25°C (36°F to 77°F) excursions permitted.
May be stored refrigerated, but must be at room temperature
before use.

The inhaler can be used for up to 7 days from the date of
first use. After 7 days of use, discard the used inhaler and
replace with a new inhaler.

PRINCIPAL DISPLAY PANEL - 64 mcg Maintenance Kit

NDC 66302-664-03
Rx ONLY

Maintenance Kit

FOR ORAL INHALATION ONLY
KIT CONTAINS:

112 cartridges, each containing
64 mcg per cartridge
+ 5
Inhalers

This MAINTENANCE KIT is NOT intended
for initial titration.

TYVASO DPI®
(treprostinil)
INHALATION
POWDER

64
mcg per
cartridge

BLISTER STORAGE
Unopened Blister Cards/Strips:
Store refrigerated at 2°C to 8°C (36°F to 46°F). Discard
unopened blister strips stored at room temperature after 8 weeks.

Opened Blister Strips:
Store at 20°C to 25°C (68°F to 77°F) with excursions permitted
to 15°C to 30°C (59°F to 86°F) [See USP Controlled Room
Temperature]. Discard opened blister strips holding unused
cartridges 3 days after opening.

INHALER STORAGE
Store at 2°C to 25°C (36°F to 77°F) excursions permitted.
May be stored refrigerated, but must be at room temperature
before use.

The inhaler can be used for up to 7 days from the date of
first use. After 7 days of use, discard the used inhaler and
replace with a new inhaler.

PRINCIPAL DISPLAY PANEL - 64 mcg Institutional Kit

NDC 66302-764-04
Rx ONLY

Institutional Kit

FOR ORAL INHALATION ONLY
KIT CONTAINS:

16 cartridges, each containing
64 mcg per cartridge
+ 2
Inhalers

This INSTITUTIONAL KIT is NOT intended
for initial titration.

TYVASO DPI®
(treprostinil)
INHALATION
POWDER

64
mcg per
cartridge

BLISTER STORAGE
Unopened Blister Cards/Strips:
Store refrigerated at 2°C to 8°C (36°F to 46°F). Discard
unopened blister strips stored at room temperature after 8 weeks.

Opened Blister Strips:
Store at 20°C to 25°C (68°F to 77°F) with excursions permitted
to 15°C to 30°C (59°F to 86°F) [See USP Controlled Room
Temperature]. Discard opened blister strips holding unused
cartridges 3 days after opening.

INHALER STORAGE
Store at 2°C to 25°C (36°F to 77°F) excursions permitted.
May be stored refrigerated, but must be at room temperature
before use.

The inhaler can be used for up to 7 days from the date of
first use. After 7 days of use, discard the used inhaler and
replace with a new inhaler.

PRINCIPAL DISPLAY PANEL - 80 mcg Maintenance Kit

NDC 66302-680-03
Rx ONLY

Maintenance Kit

FOR ORAL INHALATION ONLY
KIT CONTAINS:

112 cartridges, each containing
80 mcg per cartridge
+ 5
Inhalers

This MAINTENANCE KIT is NOT intended
for initial titration.

TYVASO DPI®
(treprostinil)
INHALATION
POWDER

80
mcg per
cartridge

BLISTER STORAGE
Unopened Blister Cards/Strips:
Store refrigerated at 2°C to 8°C (36°F to 46°F). Discard
unopened blister strips stored at room temperature after 8 weeks.

Opened Blister Strips:
Store at 20°C to 25°C (68°F to 77°F) with excursions permitted
to 15°C to 30°C (59°F to 86°F) [See USP Controlled Room
Temperature]. Discard opened blister strips holding unused
cartridges 3 days after opening.

INHALER STORAGE
Store at 2°C to 25°C (36°F to 77°F) excursions permitted.
May be stored refrigerated, but must be at room temperature
before use.

The inhaler can be used for up to 7 days from the date of
first use. After 7 days of use, discard the used inhaler and
replace with a new inhaler.

PRINCIPAL DISPLAY PANEL - 80 mcg Institutional Kit

NDC 66302-780-04
Rx ONLY

Institutional Kit

FOR ORAL INHALATION ONLY
KIT CONTAINS:

16 cartridges, each containing
80 mcg per cartridge
+ 2
Inhalers

This INSTITUTIONAL KIT is NOT intended
for initial titration.

TYVASO DPI®
(treprostinil)
INHALATION
POWDER

80
mcg per
cartridge

BLISTER STORAGE
Unopened Blister Cards/Strips:
Store refrigerated at 2°C to 8°C (36°F to 46°F). Discard
unopened blister strips stored at room temperature after 8 weeks.

Opened Blister Strips:
Store at 20°C to 25°C (68°F to 77°F) with excursions permitted
to 15°C to 30°C (59°F to 86°F) [See USP Controlled Room
Temperature]. Discard opened blister strips holding unused
cartridges 3 days after opening.

INHALER STORAGE
Store at 2°C to 25°C (36°F to 77°F) excursions permitted.
May be stored refrigerated, but must be at room temperature
before use.

The inhaler can be used for up to 7 days from the date of
first use. After 7 days of use, discard the used inhaler and
replace with a new inhaler.

PRINCIPAL DISPLAY PANEL - 16 mcg 32 mcg Titration Kit

NDC 66302-600-02
Rx ONLY

Titration Kit

FOR ORAL INHALATION ONLY
KIT CONTAINS:

112 cartridges, each containing
16 mcg per cartridge
84 cartridges, each containing
32 mcg per cartridge
+ 5
Inhalers

TYVASO DPI™
(treprostinil)
INHALATION
POWDER

16
mcg per
cartridge
32
mcg per
cartridge

BLISTER STORAGE
Unopened Blister Cards/Strips:
Store refrigerated at 2°C to 8°C (36°F to 46°F). Discard
unopened blister strips stored at room temperature after 5 weeks.

Opened Blister Strips:
Store at 20°C to 25°C (68°F to 77°F) with excursions permitted
to 15°C to 30°C (59°F to 86°F) [See USP Controlled Room
Temperature]. Discard opened blister strips holding unused
cartridges 3 days after opening.

INHALER STORAGE
Store at 2°C to 25°C (36°F to 77°F) excursions permitted.
May be stored refrigerated, but must be at room temperature
before use.

The inhaler can be used for up to 7 days from the date of
first use. After 7 days of use, discard the used inhaler and
replace with a new inhaler.

PRINCIPAL DISPLAY PANEL - 32 mcg 48 mcg Maintenance Kit

NDC 66302-620-03
Rx ONLY

Maintenance Kit

FOR ORAL INHALATION ONLY
KIT CONTAINS:

112 cartridges, each containing
32 mcg per cartridge
112 cartridges, each containing
48 mcg per cartridge
+ 5
Inhalers

This MAINTENANCE KIT is NOT intended
for initial titration.

TYVASO DPI®
(treprostinil)
INHALATION
POWDER

32
mcg per
cartridge
48
mcg per
cartridge

BLISTER STORAGE
Unopened Blister Cards/Strips:
Store refrigerated at 2°C to 8°C (36°F to 46°F). Discard
unopened blister strips stored at room temperature after 8 weeks.

Opened Blister Strips:
Store at 20°C to 25°C (68°F to 77°F) with excursions permitted
to 15°C to 30°C (59°F to 86°F) [See USP Controlled Room
Temperature]. Discard opened blister strips holding unused
cartridges 3 days after opening.

INHALER STORAGE
Store at 2°C to 25°C (36°F to 77°F) excursions permitted.
May be stored refrigerated, but must be at room temperature
before use.

The inhaler can be used for up to 7 days from the date of
first use. After 7 days of use, discard the used inhaler and
replace with a new inhaler.

PRINCIPAL DISPLAY PANEL - 32 mcg 64 mcg Maintenance Kit

NDC 66302-630-03
Rx ONLY

Maintenance Kit

FOR ORAL INHALATION ONLY
KIT CONTAINS:

112 cartridges, each containing
32 mcg per cartridge
112 cartridges, each containing
64 mcg per cartridge
+ 5
Inhalers

This MAINTENANCE KIT is NOT intended
for initial titration.

TYVASO DPI®
(treprostinil)
INHALATION
POWDER

32
mcg per
cartridge
64
mcg per
cartridge

BLISTER STORAGE
Unopened Blister Cards/Strips:
Store refrigerated at 2°C to 8°C (36°F to 46°F). Discard
unopened blister strips stored at room temperature after 8 weeks.

Opened Blister Strips:
Store at 20°C to 25°C (68°F to 77°F) with excursions permitted
to 15°C to 30°C (59°F to 86°F) [See USP Controlled Room
Temperature]. Discard opened blister strips holding unused
cartridges 3 days after opening.

INHALER STORAGE
Store at 2°C to 25°C (36°F to 77°F) excursions permitted.
May be stored refrigerated, but must be at room temperature
before use.

The inhaler can be used for up to 7 days from the date of
first use. After 7 days of use, discard the used inhaler and
replace with a new inhaler.

PRINCIPAL DISPLAY PANEL - 48 mcg 64 mcg Maintenance Kit

NDC 66302-640-03
Rx ONLY

Maintenance Kit

FOR ORAL INHALATION ONLY
KIT CONTAINS:

112 cartridges, each containing
48 mcg per cartridge
112 cartridges, each containing
64 mcg per cartridge
+ 5
Inhalers

This MAINTENANCE KIT is NOT intended
for initial titration.

TYVASO DPI®
(treprostinil)
INHALATION
POWDER

48
mcg per
cartridge
64
mcg per
cartridge

BLISTER STORAGE
Unopened Blister Cards/Strips:
Store refrigerated at 2°C to 8°C (36°F to 46°F). Discard
unopened blister strips stored at room temperature after 8 weeks.

Opened Blister Strips:
Store at 20°C to 25°C (68°F to 77°F) with excursions permitted
to 15°C to 30°C (59°F to 86°F) [See USP Controlled Room
Temperature]. Discard opened blister strips holding unused
cartridges 3 days after opening.

INHALER STORAGE
Store at 2°C to 25°C (36°F to 77°F) excursions permitted.
May be stored refrigerated, but must be at room temperature
before use.

The inhaler can be used for up to 7 days from the date of
first use. After 7 days of use, discard the used inhaler and
replace with a new inhaler.

PRINCIPAL DISPLAY PANEL - 32 mcg 48 mcg Institutional Kit

NDC 66302-720-04
Rx ONLY

Institutional Kit

FOR ORAL INHALATION ONLY
KIT CONTAINS:

16 cartridges, each containing
32 mcg per cartridge
16 cartridges, each containing
48 mcg per cartridge
+ 2
Inhalers

This INSTITUTIONAL KIT is NOT intended
for initial titration.

TYVASO DPI®
(treprostinil)
INHALATION
POWDER

32
mcg per
cartridge
48
mcg per
cartridge

BLISTER STORAGE
Unopened Blister Cards/Strips:
Store refrigerated at 2°C to 8°C (36°F to 46°F). Discard
unopened blister strips stored at room temperature after 8 weeks.

Opened Blister Strips:
Store at 20°C to 25°C (68°F to 77°F) with excursions permitted
to 15°C to 30°C (59°F to 86°F) [See USP Controlled Room
Temperature]. Discard opened blister strips holding unused
cartridges 3 days after opening.

INHALER STORAGE
Store at 2°C to 25°C (36°F to 77°F) excursions permitted.
May be stored refrigerated, but must be at room temperature
before use.

The inhaler can be used for up to 7 days from the date of
first use. After 7 days of use, discard the used inhaler and
replace with a new inhaler.

PRINCIPAL DISPLAY PANEL - 16 mcg 32 mcg 48 mcg Titration Kit

NDC 66302-610-02

Rx ONLY

Titration Kit

FOR ORAL INHALATION ONLY
KIT CONTAINS:

112 cartridges, each containing
16 mcg per cartridge

112 cartridges, each containing
32 mcg per cartridge

28 cartridges, each containing
48 mcg per cartridge

+ 5
Inhalers

TYVASO DPI®
(treprostinil)
INHALATION
POWDER

16
mcg per
cartridge

32
mcg per
cartridge

48
mcg per
cartridge

BLISTER STORAGE
Unopened Blister Cards/Strips:
Store refrigerated at 2°C to 8°C (36°F to 46°F). Discard
unopened blister strips stored at room temperature after 8 weeks.

Opened Blister Strips:
Store at 20°C to 25°C (68°F to 77°F) with excursions permitted
to 15°C to 30°C (59°F to 86°F) [See USP Controlled Room
Temperature]. Discard opened blister strips holding unused
cartridges 3 days after opening.

INHALER STORAGE
Store at 2°C to 25°C (36°F to 77°F) excursions permitted.
May be stored refrigerated, but must be at room temperature
before use.

The inhaler can be used for up to 7 days from the date of
first use. After 7 days of use, discard the used inhaler and
replace with a new inhaler.

PRINCIPAL DISPLAY PANEL - 16 mcg 48 mcg 64 mcg Maintenance Kit

NDC 66302-650-03
Rx ONLY

Maintenance Kit

FOR ORAL INHALATION ONLY
KIT CONTAINS:

112 cartridges, each containing
16 mcg per cartridge
112 cartridges, each containing
48 mcg per cartridge
112 cartridges, each containing
64 mcg per cartridge
+ 5
Inhalers

This MAINTENANCE KIT is NOT intended
for initial titration.

TYVASO DPI®
(treprostinil)
INHALATION
POWDER

16
mcg per
cartridge
48
mcg per
cartridge
64
mcg per
cartridge

BLISTER STORAGE
Unopened Blister Cards/Strips:
Store refrigerated at 2°C to 8°C (36°F to 46°F). Discard
unopened blister strips stored at room temperature after 8 weeks.

Opened Blister Strips:
Store at 20°C to 25°C (68°F to 77°F) with excursions permitted
to 15°C to 30°C (59°F to 86°F) [See USP Controlled Room
Temperature]. Discard opened blister strips holding unused
cartridges 3 days after opening.

INHALER STORAGE
Store at 2°C to 25°C (36°F to 77°F) excursions permitted.
May be stored refrigerated, but must be at room temperature
before use.

The inhaler can be used for up to 7 days from the date of
first use. After 7 days of use, discard the used inhaler and
replace with a new inhaler.

PRINCIPAL DISPLAY PANEL - 48 mcg 80 mcg Maintenance Kit

NDC 66302-660-03

Rx ONLY

Maintenance Kit

FOR ORAL INHALATION ONLY
KIT CONTAINS:

112 cartridges, each containing
48 mcg per cartridge

112 cartridges, each containing
80 mcg per cartridge

+ 5
Inhalers

This MAINTENANCE KIT is NOT intended
for initial titration.

TYVASO DPI®
(treprostinil)
INHALATION
POWDER

48
mcg per
cartridge

80
mcg per
cartridge

BLISTER STORAGE
Unopened Blister Cards/Strips:
Store refrigerated at 2°C to 8°C (36°F to 46°F). Discard
unopened blister strips stored at room temperature after 8 weeks.

Opened Blister Strips:
Store at 20°C to 25°C (68°F to 77°F) with excursions permitted
to 15°C to 30°C (59°F to 86°F) [See USP Controlled Room
Temperature]. Discard opened blister strips holding unused
cartridges 3 days after opening.

INHALER STORAGE
Store at 2°C to 25°C (36°F to 77°F) excursions permitted.
May be stored refrigerated, but must be at room temperature
before use.

The inhaler can be used for up to 7 days from the date of
first use. After 7 days of use, discard the used inhaler and
replace with a new inhaler.

PRINCIPAL DISPLAY PANEL - 64 mcg 80 mcg Maintenance Kit

NDC 66302-670-03

Rx ONLY

Maintenance Kit

FOR ORAL INHALATION ONLY
KIT CONTAINS:

112 cartridges, each containing
64 mcg per cartridge

112 cartridges, each containing
80 mcg per cartridge

+ 5
Inhalers

This MAINTENANCE KIT is NOT intended
for initial titration.

TYVASO DPI®
(treprostinil)
INHALATION
POWDER

64
mcg per
cartridge

80
mcg per
cartridge

BLISTER STORAGE
Unopened Blister Cards/Strips:
Store refrigerated at 2°C to 8°C (36°F to 46°F). Discard
unopened blister strips stored at room temperature after 8 weeks.

Opened Blister Strips:
Store at 20°C to 25°C (68°F to 77°F) with excursions permitted
to 15°C to 30°C (59°F to 86°F) [See USP Controlled Room
Temperature]. Discard opened blister strips holding unused
cartridges 3 days after opening.

INHALER STORAGE
Store at 2°C to 25°C (36°F to 77°F) excursions permitted.
May be stored refrigerated, but must be at room temperature
before use.

The inhaler can be used for up to 7 days from the date of
first use. After 7 days of use, discard the used inhaler and
replace with a new inhaler.